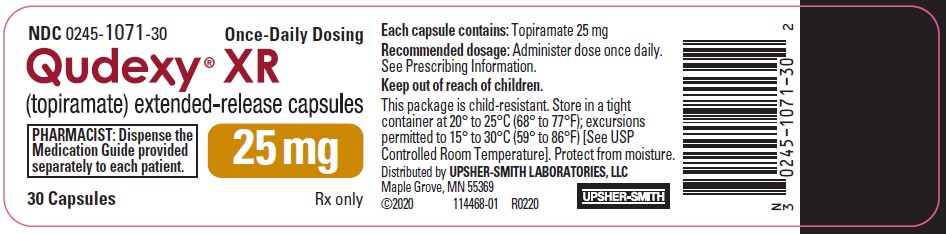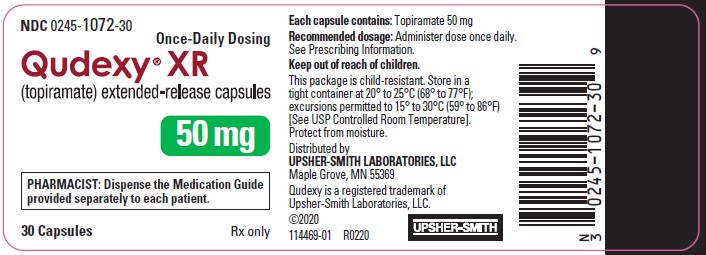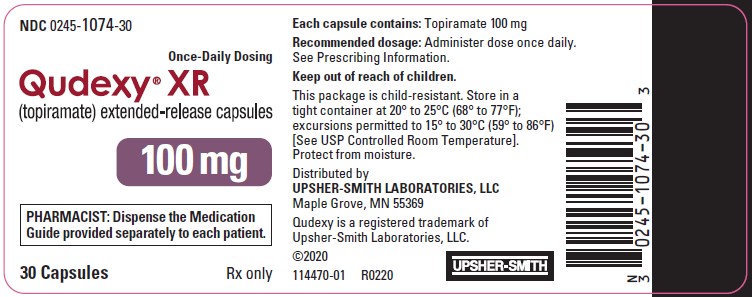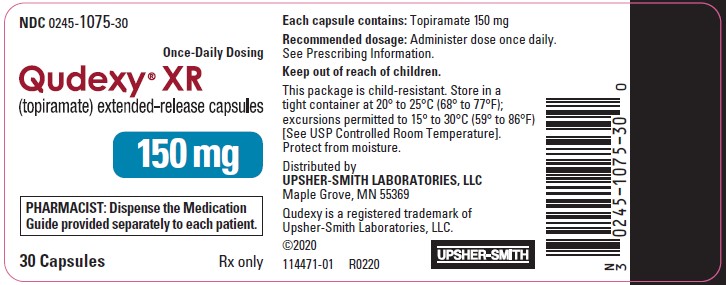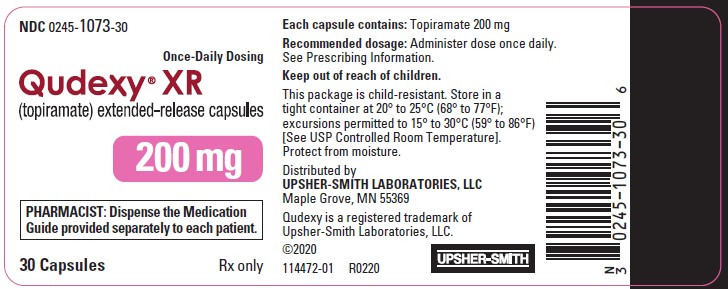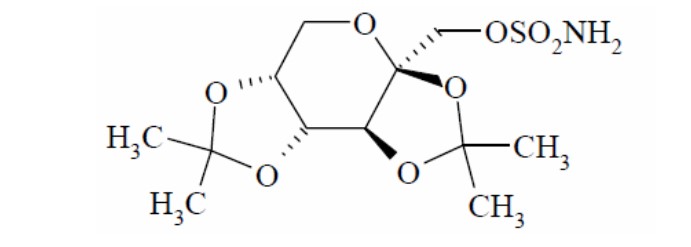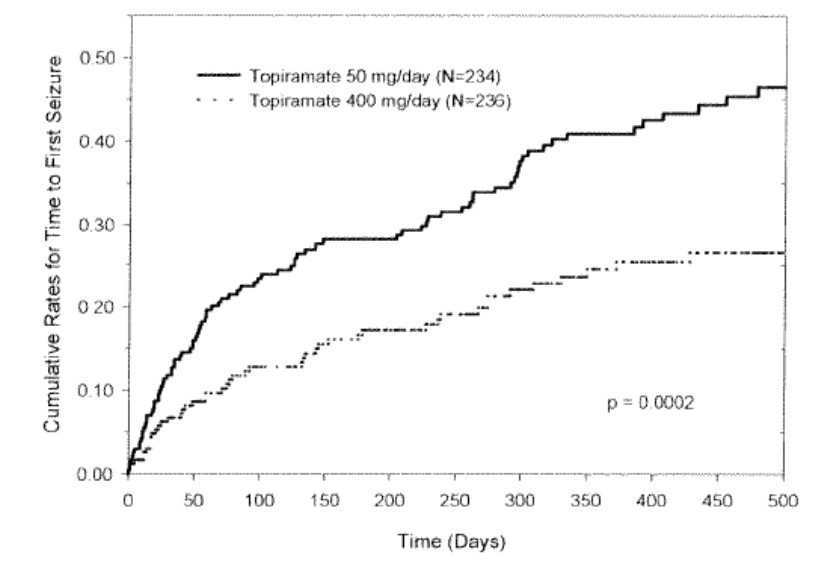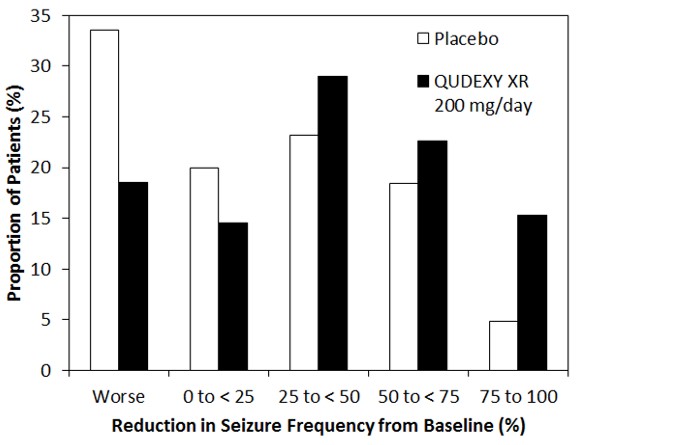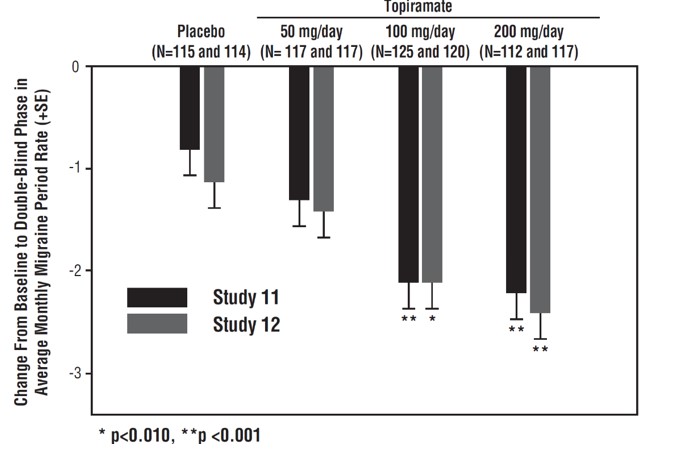 DRUG LABEL: QUDEXY

NDC: 0245-1071 | Form: CAPSULE, EXTENDED RELEASE
Manufacturer: Upsher-Smith Laboratories, LLC
Category: prescription | Type: HUMAN PRESCRIPTION DRUG LABEL
Date: 20250303

ACTIVE INGREDIENTS: TOPIRAMATE 25 mg/1 1
INACTIVE INGREDIENTS: HYPROMELLOSE 2910 (6 MPA.S); ETHYLCELLULOSE, UNSPECIFIED; DIETHYL PHTHALATE; MICROCRYSTALLINE CELLULOSE; TITANIUM DIOXIDE; FERROSOFERRIC OXIDE; FERRIC OXIDE RED

HIGHLIGHTS OF PRESCRIBING INFORMATION

These highlights do not include all the information needed to use QUDEXY®XR safely and effectively. See full prescribing information for QUDEXY®XR.
QUDEXY®XR (topiramate) extended-release capsules, for oral use
Initial U.S. Approval: 1996

1 INDICATIONS AND USAGE

QUDEXY XR is indicated for:

- Epilepsy: initial monotherapy for the treatment of partial-onset or primary generalized tonic-clonic seizures in patients 2 years of age and older (1.1); adjunctive therapy for the treatment of partial-onset seizures, primary generalized tonic-clonic seizures, or seizures associated with Lennox-Gastaut Syndrome in patients 2 years of age and older (1.2)
- Preventive treatment of migraine in patients 12 years of age and older (1.3)

2 DOSAGE AND ADMINISTRATION

- QUDEXY XR initial dose, titration, and recommended maintenance dose varies by indication and age group. See Full Prescribing Information for recommended dosage, and dosing considerations in patients with renal impairment, geriatric patients, and patients undergoing hemodialysis (2.1, 2.2, 2.3, 2.4, 2.5, 2.6)
- Capsules may be swallowed whole or opened and sprinkled on a spoonful of soft food (2.6)

3 DOSAGE FORMS AND STRENGTHS

Extended-release capsules: 25 mg, 50 mg, 100 mg, 150 mg, and 200 mg (3)

4 CONTRAINDICATIONS

None (4)

5 WARNINGS AND PRECAUTIONS

- Acute myopia and secondary angle closure glaucoma: can lead to permanent visual loss; discontinue QUDEXY XR as soon as possible (5.1)
- Visual field defects: consider discontinuation of QUDEXY XR (5.2)
- Oligohydrosis and hyperthermia: monitor decreased sweating and increased body temperature, especially in pediatric patients (5.3)
- Metabolic acidosis: baseline and periodic measurement of serum bicarbonate is recommended; consider dose reduction or discontinuation of QUDEXY XR if clinically appropriate (5.4)
- Suicidal behavior and ideation: antiepileptic drugs increase the risk of suicidal behavior or ideation (5.5)
- Cognitive/neuropsychiatric adverse reactions: use caution when operating machinery including cars; depression and mood problems may occur (5.6)
- Fetal Toxicity: use during pregnancy can cause major congenital malformations, including but not limited to cleft lip and/or palate and being small for gestational age (5.7)
- Withdrawal of AEDs: withdraw QUDEXY XR gradually (5.8)
- Decrease in Bone Mineral Density: has been shown to decrease bone mineral density and bone mineral content in pediatric patients (5.9)
- Negative effects on growth (height and weight): may slow height increase and weight gain; carefully monitor children receiving prolonged therapy (5.10)
- Serious skin reactions: If SJS or TEN is suspected, discontinue QUDEXY XR (5.11)
- Hyperammonemia/encephalopathy: measure ammonia if encephalopathic symptoms occur (5.12)
- Kidney stones: avoid use with other carbonic anhydrase inhibitors, drugs causing metabolic acidosis, or in patients on a ketogenic diet (5.13)
- Hypothermia has been reported with and without hyperammonemia during topiramate treatment with concomitant valproic acid use (5.14)

6 ADVERSE REACTIONS

Epilepsy: The most common (≥10% more frequent than placebo or low-dose topiramate) adverse reactions in adult and pediatric patients were: paresthesia, anorexia, weight loss, speech disorders/related speech problems, fatigue, dizziness, somnolence, nervousness, psychomotor slowing, abnormal vision and fever (6.1)

Migraine: Most common (≥5% more frequent than placebo) adverse reactions in adult and pediatric patients were: paresthesia, anorexia, weight loss, difficulty with memory, taste perversion, diarrhea, hypoesthesia, nausea, abdominal pain and upper respiratory tract infection (6.1)

To report SUSPECTED ADVERSE REACTIONS, contact Upsher-Smith Laboratories, LLC at 1-855-899-9180 or FDA at 1-800-FDA-1088 or www.fda.gov/medwatch

7 DRUG INTERACTIONS

- Oral contraceptives: decreased contraceptive efficacy and increased breakthrough bleeding, especially at doses greater than 200 mg per day (7.4)
- Monitor lithium levels if lithium is used with high-dose QUDEXY XR (7.7)

FULL PRESCRIBING INFORMATION

1 INDICATIONS AND USAGE

1.1 Monotherapy Epilepsy

QUDEXY XR is indicated as initial monotherapy for the treatment of partial-onset or primary generalized tonic-clonic seizures in patients 2 years of age and older.

1.2 Adjunctive Therapy Epilepsy

QUDEXY XR is indicated as adjunctive therapy for the treatment of partial-onset seizures, primary generalized tonic-clonic seizures, and seizures associated with Lennox-Gastaut Syndrome in patients 2 years of age and older.

1.3 Migraine

QUDEXY XR is indicated for the preventive treatment of migraine in patients 12 years of age and older.

2 DOSAGE AND ADMINISTRATION

2.1 Dosing in Monotherapy Epilepsy

Adults and Pediatric Patients 10 Years of Age and Older

The recommended dose for QUDEXY XR monotherapy in adults and pediatric patients 10 years of age and older is 400 mg orally once daily. Titrate QUDEXY XR according to the following schedule (see Table 1).

Table 1: Monotherapy Titration Schedule for Adults and Pediatric Patients 10 Years of Age and Older
 | QUDEXY XR Once Daily Dose
Week 1 | 50 mg
Week 2 | 100 mg
Week 3 | 150 mg
Week 4 | 200 mg
Week 5 | 300 mg
Week 6 | 400 mg

Pediatric Patients 2 to 9 Years of Age

Dosing in patients 2 to 9 years of age is based on weight. During the titration period, the initial dose of QUDEXY XR is 25 mg/day nightly for the first week. Based upon tolerability, the dosage can be increased to 50 mg/day in the second week. Dosage can be increased by 25 mg to 50 mg once daily each subsequent week, as tolerated. Titration to the minimum maintenance dose should be attempted over 5 to 7 weeks. Based upon tolerability and clinical response, additional titration to a higher dose (up to the maximum maintenance dose) can be attempted at 25 mg to 50 mg once daily weekly increments. The total daily dose should not exceed the maximum maintenance dose for each range of body weight (see Table 2).

Table 2: Monotherapy Target Total Daily Maintenance Dosing for Patients 2 to 9 Years of Age
Weight (kg) | Total Daily Dose (mg/day) Minimum Maintenance Dose | Total Daily Dose (mg/day) Maximum Maintenance Dose
Up to 11 | 150 | 250
12 to 22 | 200 | 300
23 to 31 | 200 | 350
32 to 38 | 250 | 350
Greater than 38 | 250 | 400

2.2 Dosing in Adjunctive Therapy Epilepsy

Adults (17 Years of Age and Older)

The recommended total daily dose of QUDEXY XR as adjunctive therapy in adults with partial-onset seizures or Lennox-Gastaut Syndrome is 200 mg to 400 mg orally once daily, and with primary generalized tonic-clonic seizures is 400 mg orally once daily. Initiate therapy at 25 mg to 50 mg once daily followed by titration to an effective dose in increments of 25 mg to 50 mg every week. Titrating in increments of 25 mg/day every week may delay the time to reach an effective dose. Doses above 400 mg/day have not been shown to improve responses in adults with partial-onset seizures.

Pediatric Patients 2 to 16 Years of Age

The recommended total daily dose of QUDEXY XR as adjunctive therapy for pediatric patients 2 to 16 years of age with partial-onset seizures, primary generalized tonic-clonic seizures, or seizures associated with Lennox-Gastaut syndrome is approximately 5 mg/kg to 9 mg/kg orally once daily. Begin titration at 25 mg once daily (or less, based on a range of 1 mg/kg/day to 3 mg/kg/day) given nightly for the first week. Subsequently, increase the dosage at 1- or 2-week intervals by increments of 1 mg/kg/day to 3 mg/kg/day to achieve optimal clinical response. Dose titration should be guided by clinical outcome. The total daily dose should not exceed 400 mg/day.

2.3 Dosing for the Preventive Treatment of Migraine

The recommended total daily dose of QUDEXY XR as treatment for the preventive treatment of migraine in patients 12 years of age and older is 100 mg once daily. The recommended titration rate for QUDEXY XR for the preventive treatment of migraine is as follows:

Table 3: Preventive Treatment of Migraine Titration Schedule for Patients 12 Years of Age and Older
 | QUDEXY XR Once Daily Dose
Week 1 | 25 mg
Week 2 | 50 mg
Week 3 | 75 mg
Week 4 | 100 mg

Dose and titration rate should be guided by clinical outcome. If required, longer intervals between dose adjustment can be used.

2.4 Dosing in Patients with Renal Impairment

In patients with renal impairment (creatinine clearance less than 70 mL/min/1.73 m^2), one-half of the usual adult dose of QUDEXY XR is recommended [see Use in Specific Populations (8.5, 8.6), Clinical Pharmacology (12.3)].

2.5 Dosing in Patients Undergoing Hemodialysis

To avoid rapid drops in topiramate plasma concentration during hemodialysis, a supplemental dose of QUDEXY XR may be required. The actual adjustment should take into account 1) the duration of dialysis period, 2) the clearance rate of the dialysis system being used, and 3) the effective renal clearance of topiramate in the patient being dialyzed [see Use in Specific Populations (8.7), Clinical Pharmacology (12.3)] .

2.6 Administration Instructions

QUDEXY XR capsules may be swallowed whole or may be administered by carefully opening the capsule and sprinkling the entire contents on a small amount (teaspoon) of soft food. This drug/food mixture should be swallowed immediately and not chewed or crushed. It should not be stored for further use. QUDEXY XR can be taken without regard to meals [see Clinical Pharmacology (12.3)] .

3 DOSAGE FORMS AND STRENGTHS

QUDEXY XR (topiramate) extended-release capsules are available in the following strengths and colors:

- 25 mg: light pink and grey capsules, printed with "UPSHER-SMITH" on the cap in black ink and "25 mg" on the body in black ink
- 50 mg: golden yellow and grey capsules, printed with "UPSHER-SMITH" on the cap in black ink and "50 mg" on the body in black ink
- 100 mg: reddish brown and grey capsules, printed with "UPSHER-SMITH" on the cap in black ink and "100 mg" on the body in black ink
- 150 mg: pale yellow and grey capsules, printed with "UPSHER-SMITH" on the cap in black ink and "150 mg" on the body in black ink
- 200 mg: brown and grey capsules, printed with "UPSHER-SMITH" on the cap in white ink and "200 mg" on the body in black ink

4 CONTRAINDICATIONS

None.

5 WARNINGS AND PRECAUTIONS

5.1 Acute Myopia and Secondary Angle Closure Glaucoma Syndrome

A sndrome consisting of acute myopia associated with secondary angle closure glaucoma has been reported in patients receiving topiramate. Symptoms include acute onset of decreased visual acuity and/or ocular pain. Ophthalmologic findings can include some or all of the following: myopia, mydriasis, anterior chamber shallowing, ocular hyperemia (redness), choroidal detachments, retinal pigment epithelial detachments, macular striae, and increased intraocular pressure. This syndrome may be associated with supraciliary effusion resulting in anterior displacement of the lens and iris, with secondary angle closure glaucoma. Symptoms typically occur within 1 month of initiating topiramate therapy. In contrast to primary narrow angle glaucoma, which is rare under 40 years of age, secondary angle closure glaucoma associated with topiramate has been reported in pediatric patients as well as adults. The primary treatment to reverse symptoms is discontinuation of QUDEXY XR as rapidly as possible, according to the judgment of the treating physician. Other measures, in conjunction with discontinuation of QUDEXY XR, may be helpful.

Elevated intraocular pressure of any etiology, if left untreated, can lead to serious sequelae including permanent vision loss.

5.2 Visual Field Defects

Visual field defects (independent of elevated intraocular pressure) have been reported in clinical trials and in postmarketing experience in patients receiving topiramate independent of elevated intraocular pressure. In clinical trials, most of these events were reversible after topiramate discontinuation. If visual problems occur at any time during treatment with topiramate, consideration should be given to discontinuing the drug.

5.3 Oligohydrosis and Hyperthermia

Oligohydrosis (decreased sweating), infrequently resulting in hospitalization in some cases, has been reported in association with topiramate use. Decreased sweating and an elevation in body temperature above normal characterized these cases. Some of the cases were reported after exposure to elevated environmental temperatures.

The majority of the reports have been in pediatric patients. Patients (especially pediatric patients) treated with QUDEXY XR should be monitored closely for evidence of decreased sweating and increased body temperature, especially in hot weather. Caution should be used when QUDEXY XR is prescribed with other drugs that predispose patients to heat-related disorders; these drugs include, but are not limited to, other carbonic anhydrase inhibitors and drugs with anticholinergic activity.

5.4 Metabolic Acidosis

QUDEXY XR can cause hyperchloremic, non-anion gap, metabolic acidosis (i.e., decreased serum bicarbonate below the normal reference range in the absence of chronic respiratory alkalosis). This metabolic acidosis is caused by renal bicarbonate loss due to carbonic anhydrase inhibition by QUDEXY XR. QUDEXY XR-induced metabolic acidosis can occur at any time during treatment. Bicarbonate decrements are usually mild to moderate (average decrease of 4 mEq/L at daily doses of 400 mg in adults and at approximately 6 mg/kg/day in pediatric patients); rarely, patients can experience severe decrements to values below 10 mEq/L. Conditions or therapies that predispose patients to acidosis (such as renal disease, severe respiratory disorders, status epilepticus, diarrhea, ketogenic diet or specific drugs) may be additive to the bicarbonate lowering effects of QUDEXY XR.

Metabolic acidosis was commonly observed in adult and pediatric patients treated with immediate-release topiramate in clinical trials. The incidence of decreased serum bicarbonate in pediatric trials, for adjunctive treatment of Lennox-Gastaut syndrome or refractory partial-onset seizures was as high as 67% for immediate-release topiramate (at approximately 6 mg/kg/day), and 10% for placebo. The incidence of a markedly abnormally low serum bicarbonate (i.e., absolute value < 17 mEq/L and ≥5 mEq/L decrease from pretreatment) in these trials was up to 11%, compared to ≤ 2% for placebo.

Manifestations of acute or chronic metabolic acidosis may include hyperventilation, nonspecific symptoms such as fatigue and anorexia, or more severe sequelae including cardiac arrhythmias or stupor. Chronic, untreated metabolic acidosis may increase the risk for nephrolithiasis or nephrocalcinosis and may also result in osteomalacia (referred to as rickets in pediatric patients) and/or osteoporosis with an increased risk for fractures [see Warnings and Precautions (5.9, 5.13)] . A one-year, active-controlled study of pediatric patients treated with immediate-release topiramate demonstrated that topiramate decreased lumbar spine bone mineral density and that this lumbar spine bone mineral density decrease was correlated (using change from baseline for lumbar spine Z score at final visit versus lowest post-treatment serum bicarbonate) with decreased serum bicarbonate, a reflection of metabolic acidosis [see Warnings and Precautions (5.9), Use in Specific Populations (8.4)] . Chronic metabolic acidosis in pediatric patients may also reduce growth rates, which may decrease the maximal height achieved. Long-term, open-label treatment of pediatric patients 1 to 24 months old with intractable partial epilepsy, for up to 1 year, showed reductions from baseline in length, weight, and head circumference compared to age and sex-matched normative data, although these patients with epilepsy are likely to have different growth rates than normal 1 to 24-month old patients. Reductions in length and weight were correlated to the degree of acidosis [see Use in Specific Populations (8.4)] . QUDEXY XR treatment that causes metabolic acidosis during pregnancy can possibly produce adverse effects on the fetus and might also cause metabolic acidosis in the neonate from possible transfer of topiramate to the fetus [see Warnings and Precautions (5.7), Use in Specific Populations (8.1)] .

Measurement of Serum Bicarbonate in Epilepsy and Migraine Patients

Measurement of baseline and periodic serum bicarbonate during QUDEXY XR treatment is recommended. If metabolic acidosis develops and persists, consideration should be given to reducing the dose or discontinuing QUDEXY XR (using dose tapering). If the decision is made to continue patients on QUDEXY XR in the face of persistent acidosis, alkali treatment should be considered.

5.5 Suicidal Behavior and Ideation

Antiepileptic drugs (AEDs), including QUDEXY XR increase the risk of suicidal thoughts or behavior in patients taking these drugs for any indication. Patients treated with any AED for any indication should be monitored for the emergence or worsening of depression, suicidal thoughts or behavior, and/or any unusual changes in mood or behavior.

Pooled analyses of 199 placebo-controlled clinical trials (mono- and adjunctive therapy) of 11 different AEDs showed that patients randomized to one of the AEDs had approximately twice the risk (adjusted Relative Risk 1.8, 95% CI:1.2, 2.7) of suicidal thinking or behavior compared to patients randomized to placebo. In these trials, which had a median treatment duration of 12 weeks, the estimated incidence rate of suicidal behavior or ideation among 27,863 AED-treated patients was 0.43%, compared to 0.24% among 16,029 placebo-treated patients, representing an increase of approximately one case of suicidal thinking or behavior for every 530 patients treated. There were four suicides in drug-treated patients in the trials and none in placebo-treated patients, but the number is too small to allow any conclusion about drug effect on suicide.

The increased risk of suicidal thoughts or behavior with AEDs was observed as early as one week after starting drug treatment with AEDs and persisted for the duration of treatment assessed. Because most trials included in the analysis did not extend beyond 24 weeks, the risk of suicidal thoughts or behavior beyond 24 weeks could not be assessed.

The risk of suicidal thoughts or behavior was generally consistent among drugs in the data analyzed. The finding of increased risk with AEDs of varying mechanisms of action and across a range of indications suggests that the risk applies to all AEDs used for any indication. The risk did not vary substantially by age (5 to 100 years) in the clinical trials analyzed.

Table 4 shows absolute and relative risk by indication for all evaluated AEDs.

Table 4: Risk by Indication for Antiepileptic Drugs in the Pooled Analysis
Indication | Placebo Patients with Events per 1,000 Patients | Drug Patients with Events per 1,000 Patients | Relative Risk: Incidence of Events in Drug Patients/ Incidence in Placebo Patients | Risk Difference: Additional Drug Patients with Events per 1,000 Patients
Epilepsy | 1.0 | 3.4 | 3.5 | 2.4
Psychiatric | 5.7 | 8.5 | 1.5 | 2.9
Other | 1.0 | 1.8 | 1.9 | 0.9
Total | 2.4 | 4.3 | 1.8 | 1.9

The relative risk for suicidal thoughts or behavior was higher in clinical trials for epilepsy than in clinical trials for psychiatric or other conditions, but the absolute risk differences were similar for the epilepsy and psychiatric indications.

Anyone considering prescribing QUDEXY XR or any other AED must balance the risk of suicidal thoughts or behavior with the risk of untreated illness. Epilepsy and many other illnesses for which AEDs are prescribed are themselves associated with morbidity and mortality and an increased risk of suicidal thoughts and behavior. Should suicidal thoughts and behavior emerge during treatment, the prescriber needs to consider whether the emergence of these symptoms in any given patient may be related to the illness being treated.

5.6 Cognitive/Neuropsychiatric Adverse Reactions

Immediate-release topiramate can cause cognitive/neuropsychiatric adverse reactions and therefore these are expected to be caused by QUDEXY XR. The most frequent of these can be classified into three general categories: 1) Cognitive-related dysfunction (e.g., confusion, psychomotor slowing, difficulty with concentration/attention, difficulty with memory, speech or language problems, particularly word-finding difficulties); 2) Psychiatric/behavioral disturbances (e.g., depression or mood problems); and 3) Somnolence or fatigue.

Adult Patients

Cognitive Related Dysfunction

Rapid titration rate and higher initial dose were associated with higher incidences of cognitive-related dysfunction.

In adult epilepsy adjunctive controlled trials, which used rapid titration (100 to 200 mg/day weekly increments) and target immediate-release topiramate doses of 200 mg to 1000 mg/day, 56% of patients in the 800 mg/day and 1000 mg/day dose groups experienced cognitive-related dysfunction compared to approximately 42% of patients in the 200 to 400 mg/day groups and 14% for placebo. In this rapid titration regimen, these dose-related adverse reactions began in the titration or in the maintenance phase, and in some patients these events began during titration and persisted into the maintenance phase.

In the monotherapy epilepsy-controlled trial conducted with immediate-release topiramate, the proportion of patients who experienced one or more cognitive-related adverse reactions was 19% for topiramate 50 mg per day and 26% for 400 mg per day.

In the 6-month controlled trials for the preventive treatment of migraine, which used a slower titration regimen (25 mg/day weekly increments), the proportion of patients who experienced one or more cognitive-related adverse reactions was 19% for topiramate 50 mg/day, 22% for 100 mg/day (the recommended dose), 28% for 200 mg/day, and 10% for placebo. Cognitive adverse reactions most commonly developed during titration and sometimes persisted after completion of titration.

Psychiatric/Behavioral Disturbances

Psychiatric/behavioral disturbances (e.g., depression, mood) were dose-related for both the adjunctive epilepsy and migraine populations treated with topiramate [see Warnings and Precautions (5.5)] .

Somnolence/Fatigue

Somnolence and fatigue were the adverse reactions most frequently reported during clinical trials of topiramate for adjunctive epilepsy. For the adjunctive epilepsy population, the incidence of fatigue appeared dose-related. For the monotherapy epilepsy population, the incidence of somnolence was dose-related. For the migraine population, the incidences of both somnolence and fatigue were dose-related and more common in the titration phase.

Pediatric Patients

In pediatric epilepsy trials (adjunctive and monotherapy), the incidence of cognitive/neuropsychiatric adverse reactions was generally lower than that observed in adults. These reactions included psychomotor slowing, difficulty with concentration/attention, speech disorders/related speech problems, and language problems. The most frequently reported cognitive/neuropsychiatric reactions in pediatric epilepsy patients during adjunctive therapy double-blind studies were somnolence and fatigue. The most frequently reported cognitive/neuropsychiatric reactions in pediatric epilepsy patients in the 50 mg/day and 400 mg/day groups during the monotherapy double-blind study were headache, dizziness, anorexia, and somnolence.

In pediatric migraine patients, the incidence of cognitive/neuropsychiatric adverse reactions was increased in topiramate-treated patients compared to placebo.

The risk for cognitive/neuropsychiatric adverse reactions was dose-dependent and was greatest at the highest dose (200 mg). This risk for cognitive/neuropsychiatric adverse reactions was also greater in younger patients (6 to 11 years of age) than in older patients (12 to 17 years of age). The most common cognitive/neuropsychiatric adverse reaction in these trials was difficulty with concentration/attention. Cognitive adverse reactions most commonly developed during the titration period and sometimes persisted for various durations after completion of titration.

The Cambridge Neuropsychological Test Automated Battery (CANTAB) was administered to adolescents (12 to 17 years of age) to assess the effects of topiramate on cognitive function at baseline and at the end of the Study 13 [see Clinical Studies (14.5)] . Mean change from baseline in certain CANTAB tests suggests that topiramate treatment may result in psychomotor slowing and decreased verbal fluency.

5.7 Fetal Toxicity

QUDEXY XR can cause fetal harm when administered to a pregnant woman. Data from pregnancy registries indicate that infants exposed to topiramate in uterohave an increased risk of major congenital malformation, including but not limited to cleft lip and/or cleft palate (oral clefts), and of being small for gestational age (SGA). When multiple species of pregnant animals received topiramate at clinically relevant doses, structural malformations, including craniofacial defects, and reduced fetal weights occurred in offspring [see Use in Specific Populations (8.1)] .

Consider the benefits and risks of QUDEXY XR when administering this drug in women of childbearing potential, particularly when QUDEXY XR is considered for a condition not usually associated with permanent injury or death [see Use in Specific Populations (8.1), Patient Counseling Information (17)] . QUDEXY XR should be used during pregnancy only if the potential benefit outweighs the potential risk. If this drug is used during pregnancy, or if the patient becomes pregnant while taking this drug, the patient should be informed of the potential hazard to a fetus [see Use in Specific Populations (8.1)] .

5.8 Withdrawal of Antiepileptic Drugs

In patients with or without a history of seizures or epilepsy, antiepileptic drugs, including QUDEXY XR, should be gradually withdrawn to minimize the potential for seizures or increased seizure frequency [see Clinical Studies (14)] . In situations where rapid withdrawal of QUDEXY XR is medically required, appropriate monitoring is recommended.

5.9 Decrease in Bone Mineral Density

Results of a one-year active-controlled study in pediatric patients (N=63) demonstrated negative effects of immediate-release topiramate monotherapy on bone mineral acquisition via statistically significant decreases in bone mineral density (BMD) measured in lumbar spine and in total body less head [see Use in Specific Populations (8.4)]. Twenty-one percent of immediate-release topiramate-treated patients experienced clinically important reductions in BMD (Z score change from baseline of -0.5 or greater) compared to 0 patients in the control group. Although decreases in BMD occurred across all pediatric age subgroups, patients 6 to 9 years of age were most commonly affected. The sample size and study duration were too small to determine if fracture risk is increased. Decreased BMD in the lumbar spine was correlated with decreased serum bicarbonate, which commonly occurs with topiramate treatment and reflects metabolic acidosis, a known cause of increased bone resorption [see Warnings and Precautions (5.4)] . Although small decreases in some markers of bone metabolism (e.g., serum alkaline phosphatase, calcium, phosphorus, and 1,25-dihydroxyvitamin D) occurred in immediate-release topiramate-treated patients, more significant decreases in serum parathyroid hormone and 25-hydroxyvitamin D, hormones involved in bone metabolism, were observed, along with an increased excretion of urinary calcium.

5.10 Negative Effects on Growth (Height and Weight)

Results of a one-year active-controlled study of pediatric patients (N=63) demonstrated negative effects of immediate-release topiramate monotherapy on growth (i.e., height and weight) [see Use in Specific Populations (8.4)] . Although continued growth was observed in both treatment groups, the immediate-release topiramate group showed statistically significant reductions in mean annual change from baseline in body weight compared to the control group. A similar trend of attenuation in height velocity and height change from baseline was also observed in the immediate-release topiramate group compared to the control group. Negative effects on weight and height were seen across all topiramate age subgroups. Growth (height and weight) of children receiving prolonged QUDEXY XR therapy should be carefully monitored.

5.11 Serious Skin Reactions

Serious skin reactions (Stevens-Johnson Syndrome [SJS] and Toxic Epidermal Necrolysis [TEN]) have been reported in patients receiving topiramate. QUDEXY XR should be discontinued at the first sign of a rash, unless the rash is clearly not drug-related. If signs or symptoms suggest SJS/TEN, use of this drug should not be resumed and alternative therapy should be considered. Inform patients about the signs of serious skin reactions.

5.12 Hyperammonemia and Encephalopathy (Without and With Concomitant Valproic Acid Use)

Topiramate treatment can cause hyperammonemia with or without encephalopathy [see Adverse Reactions (6.2)] . The risk for hyperammonemia with topiramate appears dose-related. Hyperammonemia has been reported more frequently when topiramate is used concomitantly with valproic acid. Post-marketing cases of hyperammonemia with or without encephalopathy have been reported with topiramate and valproic acid in patients who previously tolerated either drug alone [see Drug Interactions (7.1)] .

Clinical symptoms of hyperammonemic encephalopathy often include acute alterations in level of consciousness and/or cognitive function with lethargy and/or vomiting. In most cases, hyperammonemic encephalopathy abated with discontinuation of treatment.

The incidence of hyperammonemia in pediatric patients 12 to 17 years of age in the preventive treatment of migraine trials was 26% in patients taking topiramate monotherapy at 100 mg/day, and 14% in patients taking topiramate at 50 mg/day, compared to 9% in patients taking placebo. There was also an increased incidence of markedly increased hyperammonemia at the 100 mg dose.

Dose-related hyperammonemia was also seen in pediatric patients 1 to 24 months of age treated with topiramate and concomitant valproic acid for partial-onset epilepsy and this was not due to a pharmacokinetic interaction.

In some patients, hyperammonemia can be asymptomatic.

Monitoring for Hyperammonemia

Patients with inborn errors of metabolism or reduced hepatic mitochondrial activity may be at an increased risk for hyperammonemia with or without encephalopathy. Although not studied, topiramate treatment or an interaction of concomitant topiramate and valproic acid treatment may exacerbate existing defects or unmask deficiencies in susceptible persons.

In patients who develop unexplained lethargy, vomiting or changes in mental status associated with any topiramate treatment, hyperammonemic encephalopathy should be considered and an ammonia level should be measured.

5.13 Kidney Stones

Topiramate increases the risk of kidney stones. During adjunctive epilepsy trials, the risk for kidney stones in immediate-release topiramate-treated adults was 1.5%, an incidence about 2 to 4 times greater than expected in a similar, untreated population. As in the general population, the incidence of stone formation among topiramate-treated patients was higher in men. Kidney stones have also been reported in pediatric patients taking topiramate for epilepsy or migraine. During long-term (up to 1 year) topiramate treatment in an open-label extension study of 284 pediatric patients 1 to 24 months old with epilepsy, 7% developed kidney or bladder stones. QUDEXY XR is not approved for treatment of epilepsy in pediatric patients less than 2 years old [see Use in Specific Populations (8.4)] .

Topiramate is a carbonic anhydrase inhibitor. Carbonic anhydrase inhibitors can promote stone formation by reducing urinary citrate excretion and by increasing urinary pH [see Warnings and Precautions (5.4)] . The concomitant use of QUDEXY XR with any other drug producing metabolic acidosis, or potentially in patients on a ketogenic diet, may create a physiological environment that increases the risk of kidney stone formation, and should therefore be avoided.

Increased fluid intake increases the urinary output, lowering the concentration of substances involved in stone formation. Hydration is recommended to reduce new stone formation.

An increase in urinary calcium and a marked decrease in urinary citrate was observed in immediate-release topiramate-treated pediatric patients in one-year active-controlled study [see Use in Specific Populations (8.4)] . This increased ratio of urinary calcium/citrate increases the risk of kidney stones and/or nephrocalcinosis.

5.14 Hypothermia with Concomitant Valproic Acid Use

Hypothermia, defined as a drop-in body core temperature to <35°C (95°F), has been reported in association with topiramate use with concomitant valproic acid both in conjunction with hyperammonemia and in the absence of hyperammonemia. This adverse reaction in patients using concomitant topiramate and valproate can occur after starting topiramate treatment or after increasing the daily dose of topiramate [see Drug Interactions (7.1)] . Consideration should be given to stopping QUDEXY XR or valproate in patients who develop hypothermia, which may be manifested by a variety of clinical abnormalities including lethargy, confusion, coma, and significant alterations in other major organ systems such as the cardiovascular and respiratory systems. Clinical management and assessment should include examination of blood ammonia levels.

6 ADVERSE REACTIONS

The following serious adverse reactions are discussed in more detail in other sections of the labeling:

- Acute Myopia and Secondary Angle Closure Glaucoma [see Warnings and Precautions (5.1)]
- Visual Field Defects [see Warnings and Precautions (5.2)]
- Oligohydrosis and Hyperthermia [see Warnings and Precautions (5.3)]
- Metabolic Acidosis [see Warnings and Precautions (5.4)]
- Suicidal Behavior and Ideation [see Warnings and Precautions (5.5)]
- Cognitive/Neuropsychiatric Adverse Reactions [see Warnings and Precautions (5.6)]
- Decrease in Bone Mineral Density [see Warnings and Precautions (5.9)]
- Negative Effects on Growth (Height and Weight) [see Warnings and Precautions (5.10)]
- Serious Skin Reactions [see Warnings and Precautions (5.11)]
- Hyperammonemia and Encephalopathy (Without and With Concomitant Valproic Acid Use [see Warnings and Precautions (5.12)]
- Kidney Stones [see Warnings and Precautions (5.13)]
- Hypothermia with Concomitant Valproic Acid Use [see Warnings and Precautions (5.14)]

The data described in section 6.1 were obtained using immediate-release topiramate tablets.

6.1 Clinical Trials Experience with Immediate-Release Topiramate

Because clinical trials are conducted under widely varying conditions, adverse reaction rates observed in the clinical trials of a drug cannot be directly compared to rates in the clinical trials of another drug and may not reflect the rates observed in clinical practice.

Monotherapy Epilepsy

Adults 16 Years of Age and Older

The most common adverse reactions in the controlled trial (Study 1) that occurred in adults in the 400 mg/day topiramate group and at an incidence higher (≥ 10%) than in the 50 mg/day group were: paresthesia, weight loss, and anorexia (see Table 5) .

Approximately 21% of the 159 adult patients in the 400 mg/day group who received topiramate as monotherapy in Study 1 discontinued therapy due to adverse reactions. The most common (≥ 2% more frequent than low-dose 50 mg/day topiramate) adverse reactions causing discontinuation were difficulty with memory, fatigue, asthenia, insomnia, somnolence, and paresthesia.

Pediatric Patients 6 to 15 Years of Age

The most common adverse reactions in the controlled trial (Study 1) that occurred in pediatric patients in the 400 mg/day topiramate group and at an incidence higher (≥ 10%) than in the 50 mg/day group were fever and weight loss (see Table 5).

Approximately 14% of the 77 pediatric patients in the 400 mg/day group who received topiramate as monotherapy in the controlled clinical trial discontinued therapy due to adverse reactions. The most common (≥ 2% more frequent than in the 50 mg/day group) adverse reactions resulting in discontinuation in this trial were difficulty with concentration/attention, fever, flushing, and confusion.

Table 5 represents the incidence of adverse reactions occurring in at least 3% of the adult and pediatric patients treated with 400 mg/day immediate-release topiramate and occurring with greater incidence than 50 mg/day topiramate.

Table 5: Adverse Reactions in the High Dose Group as Compared to the Low Dose Group, in Monotherapy Epilepsy Trials (Study 1) in Adult and Pediatric Patients
 | Age Group
 | Pediatric (6 to 15 Years) |  | Adult (Age ≥16 Years)
 | Immediate-release Topiramate Daily Dosage Group (mg/day)
 | 50 | 400 | 50 | 400
Body System/ Adverse Reaction | (N=74) % | (N=77) % | (N=160) % | (N=159) %
Body as a Whole-General Disorders
Asthenia | 0 | 3 | 4 | 6
Fever | 1 | 12
Leg pain |  |  | 2 | 3
Central & Peripheral Nervous System Disorders
Paresthesia | 3 | 12 | 21 | 40
Dizziness |  |  | 13 | 14
Ataxia |  |  | 3 | 4
Hypoesthesia |  |  | 4 | 5
Hypertonia |  |  | 0 | 3
Involuntary Muscle contraction | 0 | 3
Vertigo | 0 | 3
Gastro-Intestinal System Disorders
Constipation |  |  | 1 | 4
Diarrhea | 8 | 9
Gastritis |  |  | 0 | 3
Dry mouth |  |  | 1 | 3
Liver and Biliary System Disorders
Increase in Gamma-GT |  |  | 1 | 3
Metabolic and Nutritional Disorders
Weight loss | 7 | 17 | 6 | 17
Platelet, Bleeding & Clotting Disorders
Epistaxis | 0 | 4
Psychiatric Disorders
Anorexia |  |  | 4 | 14
Anxiety |  |  | 4 | 6
Cognitive problems | 1 | 6 | 1 | 4
Confusion | 0 | 3
Depression | 0 | 3 | 7 | 9
Difficulty with concentration or attention | 7 | 10 | 7 | 8
Difficulty with memory | 1 | 3 | 6 | 11
Insomnia |  |  | 8 | 9
Decrease in libido |  |  | 0 | 3
Mood problems | 1 | 8 | 2 | 5
Personality disorder (behavior problems) | 0 | 3
Psychomotor slowing |  |  | 3 | 5
Somnolence |  |  | 10 | 15
Red Blood Cell Disorders
Anemia | 1 | 3
Reproductive Disorders, Female
Intermenstrual bleeding | 0 | 3
Vaginal hemorrhage |  |  | 0 | 3
Resistance Mechanism Disorders
Infection | 3 | 8 | 2 | 3
Viral infection | 3 | 6 | 6 | 8
Respiratory System Disorders
Bronchitis | 1 | 5 | 3 | 4
Upper respiratory tract infection | 16 | 18
Rhinitis | 5 | 6 | 2 | 4
Sinusitis | 1 | 4
Skin and Appendages Disorders
Alopecia | 1 | 4 | 3 | 4
Pruritus |  |  | 1 | 4
Rash | 3 | 4 | 1 | 4
Acne |  |  | 2 | 3
Special Senses Other, Disorders
Taste perversion |  |  | 3 | 5
Urinary System Disorders
Cystitis |  |  | 1 | 3
Micturition frequency | 0 | 3
Renal calculus |  |  | 0 | 3
Urinary incontinence | 1 | 3
Vascular (Extracardiac) Disorders
Flushing | 0 | 5

Adjunctive Therapy Epilepsy

Adults 16 Years of Age and Older

In pooled controlled clinical trials in adults with partial-onset seizures, primary generalized tonic-clonic seizures, or Lennox-Gastaut syndrome, 183 patients received adjunctive therapy with immediate-release topiramate at dosages of 200 to 400 mg/day (recommended dosage range) and 291 patients received placebo. Patients in these trials were receiving 1 to 2 concomitant antiepileptic drugs in addition to immediate-release topiramate or placebo.

The most common adverse reactions in the controlled clinical trial that occurred in adult patients in the 200 to 400 mg/day topiramate group with an incidence higher (≥ 10%) than in the placebo group were: dizziness, speech disorders/related speech problems, somnolence, nervousness, psychomotor slowing, and vision abnormal (Table 6).

Table 6 presents the incidence of adverse reactions occurring in at least 3% of adult patients treated with 200 to 400 mg/day topiramate and was greater than placebo incidence. The incidence of some adverse reactions (e.g., fatigue, dizziness, paresthesia, language problems, psychomotor slowing, depression, difficulty with concentration/attention, mood problems) was dose-related and much greater at higher than recommended topiramate dosing (i.e., 600 mg to 1000 mg daily) compared to the incidence of these adverse reactions at the recommended dosing (200 mg to 400 mg daily) range.

Table 6: Most Common Adverse Reactions in Pooled Placebo-Controlled, Adjunctive Epilepsy Trials in Adults [Patients in these adjunctive trials were receiving 1 to 2 concomitant antiepileptic drugs in addition to topiramate or placebo]
Body System/ Adverse Reaction |  | Topiramate Dosage (mg/day)
Body System/ Adverse Reaction | Placebo (N=291) | 200 to 400 (N=183)
Body as a Whole-General Disorders
Fatigue | 13 | 15
Asthenia | 1 | 6
Back pain | 4 | 5
Chest pain | 3 | 4
Influenza-like symptoms | 2 | 3
Central & Peripheral Nervous System Disorders
Dizziness | 15 | 25
Ataxia | 7 | 16
Speech disorders/Related speech problems | 2 | 13
Paresthesia | 4 | 11
Nystagmus | 7 | 10
Tremor | 6 | 9
Language problems | 1 | 6
Coordination abnormal | 2 | 4
Gait abnormal | 1 | 3
Gastro-Intestinal System Disorders
Nausea | 8 | 10
Dyspepsia | 6 | 7
Abdominal pain | 4 | 6
Constipation | 2 | 4
Metabolic and Nutritional Disorders
Weight loss | 3 | 9
Psychiatric Disorders
Somnolence | 12 | 29
Nervousness | 6 | 16
Psychomotor slowing | 2 | 13
Difficulty with memory | 3 | 12
Confusion | 5 | 11
Anorexia | 4 | 10
Difficulty with concentration/attention | 2 | 6
Mood problems | 2 | 4
Agitation | 2 | 3
Aggressive reaction | 2 | 3
Emotional lability | 1 | 3
Cognitive problems | 1 | 3
Reproductive Disorders
Breast pain | 2 | 4
Respiratory System Disorders
Rhinitis | 6 | 7
Pharyngitis | 2 | 6
Sinusitis | 4 | 5
Vision Disorders
Vision abnormal | 2 | 13
Diplopia | 5 | 10

In controlled clinical trials in adults, 11% of patients receiving immediate-release topiramate 200 to 400 mg/day as adjunctive therapy discontinued due to adverse reactions. This rate appeared to increase at dosages above 400 mg/day. Adverse reactions associated with discontinuing therapy included somnolence, dizziness, anxiety, difficulty with concentration or attention, fatigue, and paresthesia.

Pediatric Patients 2 to 15 Years of Age

In pooled, controlled clinical trials in pediatric patients (2 to 15 years of age) with partial-onset seizures, primary generalized tonic-clonic seizures, or Lennox-Gastaut syndrome, 98 patients received adjunctive therapy with immediate-release topiramate at dosages of 5 mg to 9 mg/kg/day (recommended dose range) and 101 patients received placebo.

The most common adverse reactions in the controlled clinical trial that occurred in pediatric patients in the 5 mg to 9 mg/kg/day immediate-release topiramate group with an incidence higher (≥ 10%) than in the placebo group were: fatigue and somnolence (see Table 7).

Table 7 presents the incidence of adverse reactions that occurred in at least 3% of pediatric patients 2 to 15 years of age receiving 5 mg to 9 mg/kg/day (recommended dose range) of immediate-release topiramate and was greater than placebo incidence.

Table 7: Adverse Reactions in Pooled Placebo-Controlled, Adjunctive Epilepsy Trials in Pediatric Patients 2 to 15 Years of Age [Patients in these adjunctive trials were receiving 1 to 2 concomitant antiepileptic drugs in addition to topiramate or placebo] , [Values represent the percentage of patients reporting a given adverse reaction. Patients may have reported more than one adverse reaction during the study and can be included in more than one adverse reaction category]
Body System/ | Placebo | Topiramate
Adverse Reaction | (N=101) | (N=98)
Body as a Whole-General Disorders
Fatigue | 5 | 16
Injury | 13 | 14
Central & Peripheral Nervous System Disorders
Gait abnormal | 5 | 8
Ataxia | 2 | 6
Hyperkinesia | 4 | 5
Dizziness | 2 | 4
Speech disorders/Related speech problems | 2 | 4
Gastro-Intestinal System Disorders
Nausea | 5 | 6
Saliva increased | 4 | 6
Constipation | 4 | 5
Gastroenteritis | 2 | 3
Metabolic and Nutritional Disorders
Weight loss | 1 | 9
Platelet, Bleeding, & Clotting Disorders
Purpura | 4 | 8
Epistaxis | 1 | 4
Psychiatric Disorders
Somnolence | 16 | 26
Anorexia | 15 | 24
Nervousness | 7 | 14
Personality disorder (behavior problems) | 9 | 11
Difficulty with concentration/attention | 2 | 10
Aggressive reaction | 4 | 9
Insomnia | 7 | 8
Difficulty with memory | 0 | 5
Confusion | 3 | 4
Psychomotor slowing | 2 | 3
Resistance Mechanism Disorders
Infection viral | 3 | 7
Respiratory System Disorders
Pneumonia | 1 | 5
Skin and Appendages Disorders
Skin disorder | 2 | 3
Urinary System Disorders
Urinary incontinence | 2 | 4

None of the pediatric patients who received topiramate adjunctive therapy at 5 to 9 mg/kg/day in controlled clinical trials discontinued due to adverse reactions.

Migraine

Adults

In the four multicenter, randomized, double-blind, placebo-controlled, parallel group migraine clinical trials for the preventive treatment of migraine (which included 35 adolescent patients age 12 to 15 years of age), most of the adverse reactions with topiramate were mild or moderate in severity. Most adverse reactions occurred more frequently during the titration period than during the maintenance period.

The most common adverse reactions with immediate-release topiramate 100 mg in clinical trials for the preventive treatment of migraine of predominantly adults that were seen at an incidence higher (≥5%) than in the placebo group were paresthesia, anorexia, weight loss, taste perversion, diarrhea, difficulty with memory, hypoesthesia, and nausea (see Table 8).

Table 8 includes those adverse reactions that occurred in the placebo-controlled trials where the incidence in any immediate-release topiramate treatment group was at least 3% and was greater than that for placebo patients. The incidence of some adverse reactions (e.g., fatigue, dizziness, somnolence, difficulty with memory, difficulty with concentration/attention) was dose-related and greater at higher than recommended topiramate dosing (200 mg daily) compared to the incidence of these adverse reactions at the recommended dosing (100 mg daily).

Table 8: Adverse Reactions in Pooled, Placebo-Controlled, Migraine Trials in Adults [Includes 35 adolescent patients age 12 to 15 years.] , [Values represent the percentage of patients reporting a given adverse reaction. Patients may have reported more than one adverse reaction during the study and can be included in more than one adverse reaction category.]
 |  | Topiramate Dosage (mg/day)
Body System/ | Placebo (N=445) | 50 (N=235) | 100 (N=386)
Adverse Reaction | % | % | %
Body as a Whole-General Disorders
Fatigue | 11 | 14 | 15
Injury | 7 | 9 | 6
Central & Peripheral Nervous System Disorders
Paresthesia | 6 | 35 | 51
Dizziness | 10 | 8 | 9
Hypoesthesia | 2 | 6 | 7
Language problems | 2 | 7 | 6
Gastro-Intestinal System Disorders
Nausea | 8 | 9 | 13
Diarrhea | 4 | 9 | 11
Abdominal pain | 5 | 6 | 6
Dyspepsia | 3 | 4 | 5
Dry mouth | 2 | 2 | 3
Gastroenteritis | 1 | 3 | 3
Metabolic and Nutritional Disorders
Weight loss | 1 | 6 | 9
Musculoskeletal System Disorders
Arthralgia | 2 | 7 | 3
Psychiatric Disorders
Anorexia | 6 | 9 | 15
Somnolence | 5 | 8 | 7
Difficulty with memory | 2 | 7 | 7
Insomnia | 5 | 6 | 7
Difficulty with concentration/attention | 2 | 3 | 6
Mood problems | 2 | 3 | 6
Anxiety | 3 | 4 | 5
Depression | 4 | 3 | 4
Nervousness | 2 | 4 | 4
Confusion | 2 | 2 | 3
Psychomotor slowing | 1 | 3 | 2
Reproductive Disorders, Female
Menstrual disorder | 2 | 3 | 2
Reproductive Disorders, Male
Ejaculation premature | 0 | 3 | 0
Resistance Mechanism Disorders
Viral infection | 3 | 4 | 4
Respiratory System Disorders
Upper respiratory tract infection | 12 | 13 | 14
Sinusitis | 6 | 10 | 6
Pharyngitis | 4 | 5 | 6
Coughing | 2 | 2 | 4
Bronchitis | 2 | 3 | 3
Dyspnea | 2 | 1 | 3
Skin and Appendages Disorders
Pruritis | 2 | 4 | 2
Special Sense Other, Disorders
Taste perversion | 1 | 15 | 8
Urinary System Disorders
Urinary tract infection | 2 | 4 | 2
Vision Disorders
Blurred vision [Blurred vision was the most common term considered as vision abnormal. Blurred vision was an included term that accounted for >50% of reactions coded as vision abnormal, a preferred term.] | 2 | 4 | 2

Of the 1135 patients exposed to immediate-release topiramate in the adult placebo-controlled studies, 25% discontinued due to adverse reactions, compared to 10% of the 445 placebo-treated patients. The adverse reactions associated with discontinuing therapy in the immediate-release topiramate-treated patients in these studies included paresthesia (7%), fatigue (4%), nausea (4%), difficulty with concentration/attention (3%), insomnia (3%), anorexia (2%), and dizziness (2%).

Patients treated in these studies experienced mean percent reductions in body weight that were dose-dependent. This change was not seen in the placebo group. Mean changes of 0%, -2%, -3%, and -4% were seen for the placebo group, immediate-release topiramate 50 mg, 100 mg, and 200 mg groups, respectively.

Pediatric Patients 12 to 17 Years of Age

In five, randomized, double-blind, placebo-controlled, parallel group clinical trials for the preventive treatment of migraine, most of the adverse reactions with immediate-release topiramate occurred more frequently during the titration period than during the maintenance period. Among adverse reactions with onset during titration, approximately half persisted into the maintenance period.

In four, fixed-dose, double-blind clinical trials for the preventive treatment of migraine in immediate-release topiramate-treated pediatric patients 12 to 17 years of age, the most common adverse reactions immediate-release topiramate 100 mg that were seen at an incidence higher (≥ 5%) than in the placebo group were: paresthesia, upper respiratory tract infection, anorexia, and abdominal pain (see Table 9). Table 9 shows adverse reactions from the pediatric trial [Study 13; see Clinical Studies (14.5)] in which 103 pediatric patients were treated with placebo or 50 mg or 100 mg of immediate-release topiramate, and three predominantly adult trials in which 49 pediatric patients (12 to 17 years of age) were treated with placebo or 50 mg, 100 mg, or 200 mg of immediate-release topiramate [see Clinical Studies (14.5)]. Table 9 also shows adverse reactions in pediatric patients in the controlled migraine trials when the incidence in an immediate-release topiramate dose group was at least 5% or higher and greater than the incidence of placebo. Many adverse reactions shown in Table 9 indicate a dose-dependent relationship. The incidence of some adverse reactions (e.g., allergy, fatigue, headache, anorexia, insomnia, somnolence, and viral infection) was dose-related and greater at higher than recommended immediate-release topiramate dosing (200 mg daily) compared to the incidence of these adverse reactions at the recommended dose (100 mg daily).

Table 9: Adverse Reactions in Pooled, Double-Blind Studies for the Preventive Treatment of Migraine in Pediatric Patients 12 to 17 Years of Age [35 adolescent patients aged 12 to <16 years were also included in adverse reaction assessment for adults.] , [Incidence is based on the number of subjects experiencing at least 1 adverse event, not the number of events.] , [Included studies MIG-3006, MIGR-001, MIGR-002 and MIGR-003]
 |  | Topiramate Dosage
 | Placebo | 50 mg/day | 100 mg/day
Body System/ Adverse Reaction | (N=45) % | (N=46) % | (N=48) %
Body as a Whole-General Disorders
Fatigue | 7 | 7 | 8
Fever | 2 | 4 | 6
Central & Peripheral Nervous System Disorders
Paresthesia | 7 | 20 | 19
Dizziness | 4 | 4 | 6
Gastro-Intestinal System Disorders
Abdominal pain | 9 | 7 | 15
Nausea | 4 | 4 | 8
Metabolic and Nutritional Disorders
Weight loss | 2 | 7 | 4
Psychiatric Disorders
Anorexia | 4 | 9 | 10
Somnolence | 2 | 2 | 6
Insomnia | 2 | 9 | 2
Resistance Mechanism Disorders
Infection viral | 4 | 4 | 8
Respiratory System Disorders
Upper respiratory tract infection | 11 | 26 | 23
Rhinitis | 2 | 7 | 6
Sinusitis | 2 | 9 | 4
Coughing | 0 | 7 | 2
Special Senses Other, Disorders
Taste perversion | 2 | 2 | 6
Vision Disorders
Conjunctivitis | 4 | 7 | 4

In the double-blind placebo-controlled studies, adverse reactions led to discontinuation of treatment in 8% of placebo patients compared with 6% of immediate-release topiramate-treated patients. Adverse reactions associated with discontinuing therapy that occurred in more than one immediate-release topiramate-treated patient were fatigue (1%), headache (1%), and somnolence (1%).

Increased Risk for Bleeding

Topiramate is associated with an increased risk for bleeding. In a pooled analysis of placebo-controlled studies of approved and unapproved indications, bleeding was more frequently reported as an adverse reaction for topiramate than for placebo (4.5% versus 3.0% in adult patients, and 4.4% versus 2.3% in pediatric patients). In this analysis, the incidence of serious bleeding events for topiramate and placebo was 0.3% versus 0.2% for adult patients, and 0.4% versus 0% for pediatric patients.

Adverse bleeding reactions reported with topiramate ranged from mild epistaxis, ecchymosis, and increased menstrual bleeding to life-threatening hemorrhages. In patients with serious bleeding events, conditions that increased the risk for bleeding were often present, or patients were often taking drugs that cause thrombocytopenia (other antiepileptic drugs) or affect platelet function or coagulation (e.g., aspirin, nonsteroidal anti-inflammatory drugs, selective serotonin reuptake inhibitors, or warfarin or other anticoagulants).

Other Adverse Reactions Observed During Clinical Trials

Other adverse reactions seen during clinical trials were: abnormal coordination, eosinophilia, gingival bleeding, hematuria, hypotension, myalgia, myopia, postural hypotension, scotoma, suicide attempt, syncope, and visual field defect.

Laboratory Test Abnormalities

Adult Patients

In addition to changes in serum bicarbonate (i.e., metabolic acidosis), sodium chloride and ammonia, immediate-release topiramate was associated with changes in several clinical laboratory analytes in randomized, double-blind, placebo-controlled studies [see Warnings and Precautions (5.4, 5.12)] . Controlled trials of adjunctive topiramate treatment of adults for partial-onset seizures showed an increased incidence of markedly decreased serum phosphorus (6% topiramate versus 2% placebo), markedly increased serum alkaline phosphatase (3% topiramate versus 1% placebo), and decreased serum potassium (0.4% topiramate versus 0.1% placebo).

Pediatric Patients

In pediatric patients (1 to 24 months) receiving adjunctive topiramate for partial-onset seizures, there was an increased incidence for an increased result (relative to normal analyte reference range) associated with topiramate (vs placebo) for the following clinical laboratory analytes: creatinine, BUN, alkaline phosphatase, and total protein. The incidence was also increased for a decreased result for bicarbonate (i.e., metabolic acidosis), and potassium with immediate-release (vs placebo) [see Use in Specific Populations (8.4)] . QUDEXY XR is not indicated for partial-onset seizures in pediatric patients less than 2 years of age.

In pediatric patients (ranging from 6 to 17 years of age) receiving immediate-release topiramate for the preventive treatment of migraine, there was an increased incidence for an increased result (relative to normal analyte reference range) associated with immediate-release topiramate (vs placebo) for the following clinical laboratory analytes: creatinine, BUN, uric acid, chloride, ammonia, alkaline phosphatase, total protein, platelets, and eosinophils, The incidence was also increased for a decreased result for phosphorus, bicarbonate, total white blood count, and neutrophils [see Use in Specific Populations (8.4)] . QUDEXY XR is not indicated for the preventive treatment of migraine in pediatric patients less than 12 years of age.

6.2 Clinical Trials Experience with QUDEXY XR

Because clinical trials are conducted under widely varying conditions, adverse reaction rates observed in the clinical trials of a drug cannot be directly compared to rates in the clinical trials of another drug and may not reflect the rates observed in clinical practice. In the QUDEXY XR study, a dose of 200 mg per day was administered to a limited number of patients; therefore, these results cannot be directly compared to immediate-release topiramate experience.

The safety data presented below are from 249 patients with partial epilepsy on concomitant AEDs who participated in the QUDEXY XR study [see Clinical Studies (14.4)] .

Table 10 displays the incidence of adverse reactions that occurred in ≥2% of patients and numerically greater than placebo.

Table 10: Incidence (≥2%) of Adverse Reactions in Placebo-Controlled Adjunctive Therapy Clinical Trial in Patients With Partial-Onset Seizures
Body System/ Adverse Reaction | Placebo (N=125) | QUDEXY XR (200 mg) (N=124)
General Disorders
Fatigue | 5 | 6
Asthenia | 1 | 2
Irritability | 1 | 2
Nervous System Disorders
Somnolence | 2 | 12
Dizziness | 6 | 7
Paresthesia | 2 | 7
Aphasia | 0 | 2
Dysarthria | 1 | 2
Memory impairment | 1 | 2
Psychiatric Disorder
Psychomotor retardation | 0 | 2
Cardiovascular Disorders, General
Hypertension | 1 | 3
Metabolic and Nutritional Disorders
Weight decrease | 0 | 7
Decreased appetite | 2 | 4
Anorexia | 1 | 2

In the controlled clinical study using QUDEXY XR, 8.9% of patients who received QUDEXY XR and 4.0% who received placebo discontinued as a result of adverse reactions.

6.3 Postmarketing Experience

The following adverse reactions have been identified during post-approval use of immediate-release topiramate. Because these reactions are reported voluntarily from a population of uncertain size, it is not always possible to reliably estimate their frequency or establish a causal relationship to drug exposure.

Body as a Whole–General Disorders: oligohydrosis and hyperthermia [see Warnings and Precautions (5.3)] , hyperammonemia, hyperammonemic encephalopathy [see Warnings and Precautions (5.12)] , hypothermia with concomitant valproic acid [see Warnings and Precautions (5.14)]

Gastrointestinal System Disorders: hepatic failure (including fatalities), hepatitis, pancreatitis

Skin and Appendage Disorders: bullous skin reactions (including erythema multiforme, Stevens-Johnson syndrome, toxic epidermal necrolysis) [see Warnings and Precautions (5.11)] , pemphigus

Urinary System Disorders: kidney stones, nephrocalcinosis [see Warnings and Precautions (5.4, 5.13)]

Vision Disorders: acute myopia, secondary angle closure glaucoma [see Warnings and Precautions (5.1)] , maculopathy

Hematological Disorders:decrease of the International Normalized Ratio (INR) or prothrombin time when given concomitantly with Vitamin K antagonist anticoagulant medications such as warfarin.

7 DRUG INTERACTIONS

7.1 Antiepileptic Drugs

Concomitant administration of phenytoin or carbamazepine with topiramate resulted in a clinically significant decrease in plasma concentrations of topiramate when compared to topiramate given alone. A dosage adjustment may be needed [see Clinical Pharmacology (12.3)] .

Concomitant administration of valproic acid and topiramate has been associated with hypothermia and hyperammonemia with and without encephalopathy. Examine blood ammonia levels in patients in whom the onset of hypothermia has been reported [see Warnings and Precautions (5.12, 5.14), Clinical Pharmacology (12.3)].

7.2 Other Carbonic Anhydrase Inhibitors

Concomitant use of topiramate, a carbonic anhydrase inhibitor, with any other carbonic anhydrase inhibitor (e.g., zonisamide or acetazolamide) may increase the severity of metabolic acidosis and may also increase the risk of kidney stone formation. Patients should be monitored for the appearance or worsening of metabolic acidosis when QUDEXY XR is given concomitantly with another carbonic anhydrase inhibitor [see Clinical Pharmacology (12.3)].

7.3 CNS Depressants

Concomitant administration of topiramate and alcohol or other CNS depressant drugs has not been evaluated in clinical studies. Because of the potential of topiramate to cause CNS depression, as well as other cognitive and/or neuropsychiatric adverse reactions, QUDEXY XR should be used with extreme caution if used in combination with alcohol and other CNS depressants.

7.4 Contraceptives

The possibility of decreased contraceptive efficacy and increased breakthrough bleeding may occur in patients taking contraceptive products with QUDEXY XR. Patients taking estrogen-containing or progestin-only contraceptives should be asked to report any change in their bleeding patterns. Contraceptive efficacy can be decreased even in the absence of breakthrough bleeding [see Clinical Pharmacology (12.3)] .

7.5 Hydrochlorothiazide (HCTZ)

Topiramate Cmaxand AUC increased when HCTZ was added to immediate-release topiramate. The clinical significance of this change is unknown. The addition of HCTZ to QUDEXY XR may require a decrease in the QUDEXY XR dose [see Clinical Pharmacology (12.3)] .

7.6 Pioglitazone

A decrease in the exposure of pioglitazone and its active metabolites were noted with the concurrent use of pioglitazone and immediate-release topiramate in a clinical trial. The clinical relevance of these observations is unknown; however, when QUDEXY XR is added to pioglitazone therapy or pioglitazone is added to QUDEXY XR therapy, careful attention should be given to the routine monitoring of patients for adequate control of their diabetic disease state [see Clinical Pharmacology (12.3)] .

7.7 Lithium

An increase in systemic exposure of lithium following topiramate doses of up to 600 mg/day can occur. Lithium levels should be monitored when co-administered with high-dose QUDEXY XR [see Clinical Pharmacology (12.3)] .

7.8 Amitriptyline

Some patients may experience a large increase in amitriptyline concentration in the presence of QUDEXY XR and any adjustments in amitriptyline dose should be made according to the patient's clinical response and not on the basis of plasma levels [see Clinical Pharmacology (12.3)] .

8 USE IN SPECIFIC POPULATIONS

8.1 Pregnancy

Pregnancy Exposure Registry

There is a pregnancy exposure registry that monitors pregnancy outcomes in women exposed to antiepileptic drugs (AEDs), such as QUDEXY XR, during pregnancy. Patients should be encouraged to enroll in the North American Antiepileptic Drug (NAAED) Pregnancy Registry if they become pregnant. This registry is collecting information about the safety of antiepileptic drugs during pregnancy. To enroll, patients can call the toll-free number 1-888-233-2334. Information about the North American Drug Pregnancy Registry can be found at http://www.aedpregnancyregistry.org/.

Risk Summary

QUDEXY XR can cause fetal harm when administered to a pregnant woman. Data from pregnancy registries indicate that infants exposed to topiramate in uterohave increased risk of major congenital malformations, including but not limited to cleft lip and/or cleft palate (oral clefts) and of being small for gestational age (SGA) [see Human Data]. SGA has been observed at all doses and appears to be dose-dependent. The prevalence of SGA is greater in infants of women who received higher doses of topiramate during pregnancy. In addition, the prevalence of SGA in infants of women who continued topiramate use until later in pregnancy is higher compared to the prevalence in infants of women who stopped topiramate use before the third trimester.

In multiple animal species, topiramate demonstrated developmental toxicity, including increased incidences of fetal malformations, in the absence of maternal toxicity at clinically relevant doses [see Animal Data] .

All pregnancies have a background risk of birth defects, loss, or other adverse outcomes. The estimated background risk of major birth defects and miscarriage for the indicated population is unknown. In the U.S. general population, the estimated background risks of major birth defects and miscarriage in clinically recognized pregnancies are 2% to 4% and 15% to 20%, respectively.

Clinical Considerations

Fetal/Neonatal Adverse Reactions

Consider the benefits and risks of topiramate when prescribing this drug to women of childbearing potential, particularly when topiramate is considered for a condition not usually associated with permanent injury or death. Because of the risk of oral clefts to the fetus, which occur in the first trimester of pregnancy before many women know they are pregnant, all women of childbearing potential should be informed of the potential risk to the fetus from exposure to topiramate. Women who are planning a pregnancy should be counseled regarding the relative risks and benefits of topiramate use during pregnancy, and alternative therapeutic options should be considered for these patients.

Labor or Delivery

Although the effect of topiramate on labor and delivery in humans has not been established, the development of topiramate-induced metabolic acidosis in the mother and/or in the fetus might affect the fetus' ability to tolerate labor .

QUDEXY XR treatment can cause metabolic acidosis [see Warnings and Precautions (5.4)]. The effect of topiramate-induced metabolic acidosis has not been studied in pregnancy; however, metabolic acidosis in pregnancy (due to other causes) can cause decreased fetal growth, decreased fetal oxygenation, and fetal death, and may affect the fetus' ability to tolerate labor. Pregnant patients should be monitored for metabolic acidosis and treated as in the nonpregnant state [see Warnings and Precautions (5.4)]. Newborns of mothers treated with QUDEXY XR should be monitored for metabolic acidosis because of transfer of topiramate to the fetus and possible occurrence of transient metabolic acidosis following birth.

Based on limited information, topiramate has also been associated with pre-term labor and premature delivery.

Data

Human Data

Data from pregnancy registries indicate an increased risk of major congenital malformations, including but not limited to oral clefts in infants exposed to topiramate during the first trimester of pregnancy. Other than oral clefts, no specific pattern of major congenital malformations or grouping of major congenital malformation types were observed. In the NAAED pregnancy registry, when topiramate-exposed infants with only oral clefts were excluded, the prevalence of major congenital malformations (4.1%) was higher than that in infants exposed to a reference AED (1.8%) or in infants with mothers without epilepsy and without exposure to AEDs (1.1%). The prevalence of oral clefts among topiramate-exposed infants (1.4%) was higher than the prevalence in infants exposed to a reference AED (0.3%) or the prevalence in infants with mothers without epilepsy and without exposure to AEDs (0.11%). It was also higher than the background prevalence in the United States (0.17%) as estimated by the Centers for Disease Control and Prevention (CDC). The relative risk of oral clefts in topiramate-exposed pregnancies in the NAAED Pregnancy Registry was 12,5 (95% Confidence Interval=[CI] 5.9 to 26.7) as compared to the risk in a background population of untreated women. The UK Epilepsy and Pregnancy Register reported a prevalence of oral clefts among infants exposed to topiramate monotherapy (3.2%) that was 16 times higher than the background rate in the UK (0.2%).

Data from the NAAED pregnancy registry and a population-based birth registry cohort indicate that exposure to topiramate in uterois associated with an increased risk of SGA newborns (birth weight <10th percentile). In the NAAED pregnancy registry, 19.7% of topiramate-exposed newborns were SGA compared to 7.9% of newborns exposed to a reference AED, and 5.4% of newborns of mothers without epilepsy and without AED exposure. In the Medical Birth Registry of Norway (MBRN), a population-based pregnancy registry, 25% of newborns in the topiramate monotherapy exposure group were SGA compared to 9% in the comparison group who were unexposed to AEDs. The long-term consequences of the SGA findings are not known.

Animal Data

When topiramate (0, 20, 100, or 500 mg/kg/day) was administered orally to pregnant mice during the period of organogenesis, the incidence of fetal malformations (primarily craniofacial defects) were increased at all doses. Fetal body weights and skeletal ossification were reduced at the highest dose tested in conjunction with decreased maternal body weight gain. A no-effect dose for embryofetal developmental toxicity in mice was not identified. The lowest dose tested, which was associated with an increased incidence of malformations, is less than the maximum recommended human dose (MRHD) for epilepsy (400 mg/day) or migraine (100 mg/day) on a body surface area (mg/m^2) basis.

In pregnant rats administered topiramate (0, 20, 100, and 500 mg/kg/day or 0, 0.2, 2.5, 30, and 400 mg/kg/day) orally during the period of organogenesis, the frequency of limb malformations (ectrodactyly, micromelia, and amelia) was increased in fetuses at 400 and 500 mg/kg/day. Embryotoxicity (reduced fetal body weights, increased incidences of structural variations) was observed at doses as low as 20 mg/kg/day. Clinical signs of maternal toxicity were seen at 400 mg/kg/day and above, and maternal body weight gain was reduced at doses of 100 mg/kg/day or greater. The no-effect dose (2.5 mg/kg/day) for embryofetal developmental toxicity in rats is less than the MRHD for epilepsy or migraine on a mg/m^2basis.

In pregnant rabbits administered topiramate (0, 20, 60, and 180 mg/kg/day or 0, 10, 35, and 120 mg/kg/day) orally during organogenesis, embryofetal mortality was increased at 35 mg/kg/day and an increased incidence of fetal malformations (primarily rib and vertebral malformations) was observed at 120 mg/kg/day. Evidence of maternal toxicity (decreased body weight gain, clinical signs, and/or mortality) was seen at 35 mg/kg/day and above. The no-effect dose (20 mg/kg/day) for embryofetal developmental toxicity in rabbits is equivalent to the MRHD for epilepsy and approximately 4 times the MRHD for migraine on a mg/m^2basis.

When topiramate (0, 0.2, 4, 20, and 100 mg/kg/day or 0, 2, 20, and 200 mg/kg/day) was administered orally to female rats during the latter part of gestation and throughout lactation, offspring exhibited decreased viability and delayed physical development at 200 mg/kg/day and reductions in pre- and/or postweaning body weight gain at 2 mg/kg/day and above. Maternal toxicity (decreased body weight gain, clinical signs) was evident at 100 mg/kg/day or greater. In a rat embryofetal development study which included postnatal assessment of offspring, oral administration of topiramate (0, 0.2, 2.5, 30, and 400 mg/kg/day) to pregnant animals during the period of organogenesis resulted in delayed physical development in offspring at 400 mg/kg/day and persistent reductions in body weight gain in offspring at 30 mg/kg/day and higher. The no-effect dose (0.2 mg/kg/day) for pre- and postnatal developmental toxicity in rats is less than the MRHD for epilepsy or migraine on a mg/m^2basis.

8.2 Lactation

Risk Summary

Topiramate is excreted in human milk [see Data]. The effects of topiramate on milk production are unknown. Diarrhea and somnolence have been reported in breastfed infants whose mothers receive topiramate treatment.

The developmental and health benefits of breastfeeding should be considered along with the mother's clinical need for QUDEXY XR and any potential adverse effects on the breastfed infant from QUDEXY XR or from the underlying maternal condition.

Data

Human Data

Limited data from 5 women with epilepsy treated with topiramate during lactation showed drug levels in milk similar to those in maternal plasma.

8.3 Females and Males of Reproductive Potential

Contraception

Women of childbearing potential who are not planning a pregnancy should use effective contraception because of the risk of major congenital malformations, including oral clefts, and the risk of infants being SGA [see Drug Interactions (7.4), and Use in Specific Populations (8.1)].

8.4 Pediatric Use

Adjunctive Treatment for Epilepsy

Pediatric Patients 2 Years of Age and Older

The safety and effectiveness of QUDEXY XR as adjunctive therapy for the treatment of partial-onset seizures, primary generalized tonic-clonic seizures, or seizures associated with Lennox-Gastaut syndrome have been established in pediatric patients 2 years of age and older and is based on controlled trials with immediate-release topiramate [see Adverse Reactions (6.1)and Clinical Studies (14.3, 14.4)] .

The adverse reactions (both common and serious) in pediatric patients are similar to those seen in adults [see Warnings and Precautions (5)and Adverse Reactions (6)] .

These include, but are not limited to:

- oligohydrosis and hyperthermia [see Warnings and Precautions (5.3)]
- dose-related increased incidence of metabolic acidosis [see Warnings and Precautions (5.4)]
- dose-related increased incidence of hyperammonemia [see Warnings and Precautions (5.12)]

Pediatric Patients Below the Age of 2 Years

The following pediatric use information is based on studies conducted with immediate-release topiramate.

Safety and effectiveness in patients below the age of 2 years have not been established for the adjunctive therapy treatment of partial-onset seizures, primary generalized tonic-clonic seizures, or seizures associated with Lennox-Gastaut syndrome. In a single randomized, double-blind, placebo-controlled investigational trial, the efficacy, safety, and tolerability of immediate-release topiramate oral liquid and sprinkle formulations as an adjunct to concurrent antiepileptic drug therapy in pediatric patients 1 to 24 months of age with refractory partial-onset seizures were assessed. After 20 days of double-blind treatment, immediate-release topiramate (at fixed doses of 5, 15, and 25 mg/kg/day) did not demonstrate efficacy compared with placebo in controlling seizures.

In general, the adverse reaction profile for immediate-release topiramate in this population was similar to that of older pediatric patients, although results from the above controlled study and an open-label, long-term extension study in these pediatric patients 1 to 24 months old suggested some adverse reactions/toxicities not previously observed in older pediatric patients and adults; i.e., growth/length retardation, certain clinical laboratory abnormalities, and other adverse reactions/toxicities that occurred with a greater frequency and/or greater severity than had been recognized previously from studies in older pediatric patients or adults for various indications.

These very young pediatric patients appeared to experience an increased risk for infections (any topiramate dose 12%, placebo 0%) and of respiratory disorders (any topiramate dose 40%, placebo 16%). The following adverse reactions were observed in at least 3% of patients on immediate-release topiramate and were 3% to 7% more frequent than in patients on placebo: viral infection, bronchitis, pharyngitis, rhinitis, otitis media, upper respiratory infection, cough, and bronchospasm. A generally similar profile was observed in older pediatric patients [see Adverse Reactions (6.1)] .

Immediate-release topiramate resulted in an increased incidence of patients with increased creatinine (any topiramate dose 5%, placebo 0%), BUN (any topiramate dose 3%, placebo 0%), and protein (any topiramate dose 34%, placebo 6%), and an increased incidence of decreased potassium (any topiramate dose 7%, placebo 0%). This increased frequency of abnormal values was not dose-related. Creatinine was the only analyte showing a noteworthy increased incidence (topiramate 25 mg/kg/day 5%, placebo 0%) of a markedly abnormal increase [see Adverse Reactions (6.1)] . The significance of these findings is uncertain.

Immediate-release topiramate treatment also produced a dose-related increase in the percentage of patients who had a shift from normal at baseline to high/increased (above the normal reference range) in total eosinophil count at the end of treatment. The incidence of these abnormal shifts was 6% for placebo, 10% for 5 mg/kg/day, 9% for 15 mg/kg/day, 14% for 25 mg/kg/day, and 11% for any topiramate dose [see Adverse Reactions (6.1)] . There was a mean dose-related increase in alkaline phosphatase. The significance of these findings is uncertain.

Topiramate produced a dose-related increased incidence of hyperammonemia [see Warnings and Precautions (5.12)].

Treatment with immediate-release topiramate for up to 1 year was associated with reductions in Z SCORES for length, weight, and head circumference [see Warnings and Precautions (5.4), Adverse Reactions (6.1)] .

In open-label, uncontrolled experience, increasing impairment of adaptive behavior was documented in behavioral testing over time in this population. There was a suggestion that this effect was dose-related. However, because of the absence of an appropriate control group, it is not known if this decrement in function was treatment related or reflects the patient's underlying disease (e.g., patients who received higher doses may have more severe underlying disease) [see Warnings and Precautions (5.6)] .

In this open-label, uncontrolled study, the mortality was 37 deaths/1,000 patient years. It is not possible to know whether this mortality rate is related to immediate-release topiramate treatment, because the background mortality rate for a similar, significantly refractory, young pediatric population (1 to 24 months) with partial epilepsy is not known.

Monotherapy Treatment Epilepsy

Pediatric Patients 2 Years of Age and Older

The safety and effectiveness of QUDEXY XR as monotherapy for the treatment of partial-onset seizures or primary generalized tonic-clonic seizures have been established in pediatric patients aged 2 years and older and is based on controlled trials with immediate-release topiramate [see Adverse Reactions (6.1), Clinical Studies (14.1)] .

A one-year, active-controlled, open-label study with blinded assessments of bone mineral density (BMD) and growth in pediatric patients 4 to 15 years of age, including 63 patients with recent or new onset of epilepsy, was conducted to assess effects of immediate-release topiramate (N=28, 6 to 15 years of age) versus levetiracetam (N=35, 4 to 15 years of age) monotherapy on bone mineralization and on height and weight, which reflect growth. Effects on bone mineralization were evaluated via dual-energy X-ray absorptiometry and blood markers. Table 11 summarizes effects of immediate-release topiramate at 12 months for key safety outcomes including BMD, height, height velocity, and weight. All Least Square Mean values for immediate-release topiramate and the comparator were positive. Therefore, the Least Square Mean treatment differences shown reflect a topiramate induced attenuation of the key safety outcomes. Statistically significant effects were observed for decreases in BMD (and bone mineral content) in lumbar spine and total body less head and in weight. Subgroup analyses according to age demonstrated similar negative effects for all key safety outcomes (i.e., BMD, height, weight).

Table 11: Summary of Immediate-Release Topiramate Treatment Difference Results at 12 Months for Key Safety Outcomes
Safety Parameter | Treatment Difference in Least Square Means (95 % Confidence Interval)
Annual Change in BMD Lumbar Spine (g/cm^2) | -0.036 (-0.058, -0.014)
Annual Change in BMD TBLH [TBLH = total body less head] (g/cm^2) | -0.026 (-0.039, -0.012)
Annual Change in Height (cm) (4 to 9 years, Primary Analysis Population for Height) [Whereas no patients were randomized to 2 to 5 year of age subgroup for immediate-release topiramate, 5 patients (4 to 5 years) were randomized to the active control group.] | -0.84 (-2.67, 0.99)
Annual Change in Height (cm) (4 to 15 years) | -0.75 (-2.21, 0.71)
Annual Change in Height (cm) (10 to 15 years) | -1.01 (-3.64, 1.61)
Height Velocity (cm/year) (4 to 9 years) | 1.00 (-2.76, 0.76)
Height Velocity (cm/year) (4 to 15 years) | -0.98 (-2.33, 0.37)
Height Velocity (cm/year) (10 to 15 years) | -0.96 (-3.24, 1.32)
Annual Change in Weight (kg) | -2.05 (-3.66, -0.45)

Metabolic acidosis (serum bicarbonate < 20 mEq/L) was observed in all immediate-release topiramate-treated patients at some time in the study [see Warnings and Precautions (5.4)] . Over the whole study, 76% more immediate-release topiramate -treated patients experienced persistent metabolic acidosis (i.e., 2 consecutive visits with or final serum bicarbonate < 20 mEq/L) compared to levetiracetam treated patients. Over the whole study, 35% more immediate-release topiramate-treated patients experienced a markedly abnormally low serum bicarbonate (i.e., absolute value < 17 mEq/L and ≥ 5 mEq/L decrease from pre-treatment), indicating the frequency of more severe metabolic acidosis, compared to levetiracetam-treated patients. The decrease in BMD at 12 months was correlated with decreased serum bicarbonate, suggesting that metabolic acidosis was at least a partial factor contributing to this adverse effect on BMD.

Immediate-release topiramate-treated patients exhibited an increased risk for developing an increased serum creatinine and an increased serum glucose above the normal reference range compared to control patients.

Pediatric Patients Below the Age of 2 Years

Safety and effectiveness in patients below the age of 2 years have not been established for the monotherapy treatment of epilepsy.

Preventive Treatment of Migraine

Pediatric Patients 12 to 17 Years of Age

Safety and effectiveness of topiramate for the preventive treatment of migraine was studied in 5 double-blind, randomized, placebo-controlled, parallel-group trials in a total of 219 pediatric patients, at doses of 50 to 200 mg/day, or 2 to 3 mg/kg/day. These comprised a fixed dose study in 103 pediatric patients 12 to 17 years of age [see Clinical Studies (14.5)] , a flexible dose (2 to 3 mg/kg/day), placebo-controlled study in 157 pediatric patients 6 to 16 years of age (including 67 pediatric patients 12 to 16 years of age), and a total of 49 pediatric patients 12 to 17 years of age in 3 studies for the preventive treatment of migraine primarily in adults. Open-label extension phases of 3 studies enabled evaluation of long-term safety for up to 6 months after the end of the double-blind phase.

Efficacy of topiramate for the preventive treatment of migraine in pediatric patients 12 to 17 years of age is demonstrated for a 100 mg daily dose in Study 13 [see Clinical Studies (14.5)]. Efficacy of topiramate (2 to 3 mg/kg/day) for the preventive treatment of migraine was not demonstrated in a placebo-controlled trial of 157 pediatric patients (6 to 16 years of age) that included treatment of 67 pediatric patients (12 to 16 years of age) for 20 weeks.

In the pediatric trials (12 to 17 years of age) in which patients were randomized to placebo or a fixed daily dose of immediate-release topiramate, the most common adverse reactions with immediate-release topiramate that were seen at an incidence higher (≥ 5%) than in the placebo group were: paresthesia, upper respiratory tract infection, anorexia, and abdominal pain [see Adverse Reactions (6.1)] .

The most common cognitive adverse reaction in pooled double-blind studies in pediatric patients 12 to 17 years of age was difficulty with concentration/attention [see Warnings and Precautions (5.6)].

Markedly abnormally low serum bicarbonate values indicative of metabolic acidosis were reported in topiramate-treated pediatric migraine patients [see Warnings and Precautions (5.4)] .

In topiramate-treated pediatric patients (12 to 17 years of age) compared to placebo-treated patients, abnormally increased results were more frequent for creatinine, BUN, uric acid, chloride, ammonia, total protein, and platelets. Abnormally decreased results were observed with topiramate vs placebo treatment for phosphorus and bicarbonate [see Warnings and Precautions (5.4)and Adverse Reactions (6.1)] .

Notable changes (increases and decreases) from baseline in systolic blood pressure, diastolic blood pressure, and pulse were observed occurred more commonly in pediatric patients treated with topiramate compared to pediatric patients treated with placebo [see Clinical Pharmacology (12.2)].

Pediatric Patients Below the Age of 12 Years

Safety and effectiveness in pediatric patients below the age of 12 years have not been established for the preventive treatment of migraine.

In a double-blind study in 90 pediatric patients 6 to 11 years of age (including 59 topiramate-treated and 31 placebo patients), the adverse reaction profile was generally similar to that seen in pooled double-blind studies of pediatric patients 12 to 17 years of age. The most common adverse reactions that occurred in immediate-release topiramate-treated pediatric patients 6 to 11 years of age, and at least twice as frequently than placebo, were gastroenteritis (12% topiramate, 6% placebo), sinusitis (10% topiramate, 3% placebo), weight loss (8% topiramate, 3% placebo) and paresthesia (7% topiramate, 0% placebo). Difficulty with concentration/attention occurred in 3 topiramate-treated patients (5%) and 0 placebo-treated patients.

The risk for cognitive adverse reaction was greater in younger patients (6 to 11 years of age) than in older patients (12 to 17 years of age) [see Warnings and Precautions (5.6)] .

Juvenile Animal Studies

When topiramate (0, 30, 90 or 300 mg/kg/day) was administered orally to rats during the juvenile period of development (postnatal days 12 to 50), bone growth plate thickness was reduced in males at the highest dose, which is approximately 5 to 8 times the maximum recommended pediatric dose (9 mg/kg/day) on a body surface area (mg/m^2) basis.

8.5 Geriatric Use

Clinical studies of immediate-release topiramate did not include sufficient numbers of subjects age 65 and over to determine whether they respond differently than younger subjects. Dosage adjustment may be necessary for elderly with creatinine clearance less than 70 mL/min/1.73 m^2. Estimate GFR should be measured prior to dosing [see Dosage and Administration (2.3)and Clinical Pharmacology (12.3)] .

8.6 Renal Impairment

The clearance of topiramate is reduced in patients with moderate (creatinine clearance 30 to 69 mL/min/1.73 m^2) and severe (creatinine clearance less than 30 mL/min/1.73 m^2) renal impairment. A dosage adjustment is recommended in patients with moderate or severe renal impairment [see Dosage and Administration (2.4)and Clinical Pharmacology (12.3)] .

8.7 Patients Undergoing Hemodialysis

Topiramate is cleared by hemodialysis at a rate that is 4 to 6 times greater than in a normal individual. A dosage adjustment may be required [see Dosage and Administration (2.5)and Clinical Pharmacology (12.3)] .

10 OVERDOSAGE

Overdoses of topiramate have been reported. Signs and symptoms included convulsions, drowsiness, speech disturbance, blurred vision, diplopia, impaired mentation, lethargy, abnormal coordination, stupor, hypotension, abdominal pain, agitation, dizziness and depression. The clinical consequences were not severe in most cases, but deaths have been reported after overdoses involving topiramate.

Topiramate overdose has resulted in severe metabolic acidosis [see Warnings and Precautions (5.4)] .

A patient who ingested a dose of immediate-release topiramate between 96 g and 110 g was admitted to a hospital with a coma lasting 20 to 24 hours followed by full recovery after 3 to 4 days.

Similar signs, symptoms, and clinical consequences are expected to occur with overdosage of QUDEXY XR. Therefore, in the event of QUDEXY XR overdose, QUDEXY XR should be discontinued and general supportive treatment given until clinical toxicity has been diminished or resolved.

Hemodialysis is an effective means of removing topiramate from the body.

11 DESCRIPTION

Topiramate, USP, is a sulfamate-substituted monosaccharide. QUDEXY XR (topiramate) extended-release capsules are available as 25 mg, 50 mg, 100 mg, 150 mg, and 200 mg capsules for oral administration as whole capsules or opened and sprinkled onto a spoonful of soft food.

Topiramate is a white to off-white powder. Topiramate is freely soluble in polar organic solvents such as acetonitrile and acetone; and very slightly soluble to practically insoluble in non-polar organic solvents such as hexanes. Topiramate has the molecular formula C12H21NO8S and a molecular weight of 339.4. Topiramate is designated chemically as 2,3:4,5-Di-O-isopropylidene-β-D-fructopyranose sulfamate and has the following structural formula:

QUDEXY XR (topiramate) extended-release capsules contain beads of topiramate in a capsule. The inactive ingredients are microcrystalline cellulose, hypromellose 2910, ethylcellulose, diethyl phthalate.

In addition, the capsule shells for all strengths contain hypromellose 2910, titanium dioxide, black iron oxide, red iron oxide and/or yellow iron oxide, black pharmaceutical ink, and white pharmaceutical ink (200 mg only).

12 CLINICAL PHARMACOLOGY

12.1 Mechanism of Action

The precise mechanisms by which topiramate exerts its anticonvulsant and preventive migraine effects are unknown; however, preclinical studies have revealed four properties that may contribute to topiramate's efficacy for epilepsy and the preventive treatment of migraine. Electrophysiological and biochemical evidence suggests that topiramate, at pharmacologically relevant concentrations, blocks voltage-dependent sodium channels, augments the activity of the neurotransmitter gamma-aminobutyrate at some subtypes of the GABA-A receptor, antagonizes the AMPA/kainate subtype of the glutamate receptor, and inhibits the carbonic anhydrase enzyme, particularly isozymes II and IV.

12.2 Pharmacodynamics

Topiramate has anticonvulsant activity in rat and mouse maximal electroshock seizure (MES) tests. Topiramate is only weakly effective in blocking clonic seizures induced by the GABA-A receptor antagonist, pentylenetetrazole. Topiramate is also effective in rodent models of epilepsy, which include tonic and absence-like seizures in the spontaneous epileptic rat (SER) and tonic and clonic seizures induced in rats by kindling of the amygdala or by global ischemia.

Changes (increases and decreases) from baseline in vital signs (systolic blood pressure-SBP, diastolic blood pressure-DBP, pulse) occurred more frequently in pediatric patients (6 to 17 years) treated with various daily doses of topiramate (50 mg, 100 mg, 200 mg, 2 to 3 mg/kg) than in patients treated with placebo in controlled trials for the preventive treatment of migraine. The most notable changes were SBP < 90 mm Hg, DBP < 50 mm Hg, SBP or DBP increases or decreases ≥ 20 mm Hg, and pulse increases or decreases ≥ 30 beats per minute. These changes were often dose-related and were most frequently associated with the greatest treatment difference at the 200 mg dose level. Systematic collection of orthostatic vital signs has not been conducted. The clinical significance of these various changes in vital signs has not been clearly established.

12.3 Pharmacokinetics

Absorption and Distribution

The pharmacokinetics of QUDEXY XR are linear with dose proportional increases in plasma concentration when administered as a single oral dose over the range of 50 mg to 1,400 mg. At 25 mg, the pharmacokinetics of QUDEXY XR are nonlinear, possibly due to the binding of topiramate to carbonic anhydrase in red blood cells.

QUDEXY XR sprinkled on a spoonful of soft food is bioequivalent to the intact capsule formulation.

Following a single 200 mg oral dose of QUDEXY XR, peak plasma concentrations (Tmax) occurred approximately 20 hours after dosing. Steady-state was reached in about 5 days following daily dosing of QUDEXY XR in subjects with normal renal function, with a Tmaxof approximately 6 hours.

At steady-state, the plasma exposure (AUC0–24hr, Cmax, and Cmin) of topiramate from QUDEXY XR administered once daily and the immediate-release topiramate tablets administered twice-daily were shown to be bioequivalent. Fluctuation of topiramate plasma concentrations at steady-state for QUDEXY XR administered once daily was approximately 40% in healthy subjects, compared to approximately 53% for immediate-release topiramate [see Clinical Pharmacology (12.6)] .

Compared to the fasted state, high-fat meal had no effect on bioavailability (AUC and Cmax) but delayed the Tmaxby approximately 4 hours following a single dose of QUDEXY XR. QUDEXY XR can be taken without regard to meals.

Topiramate is 15% to 41% bound to human plasma proteins over the blood concentration range of 0.5 mcg/mL to 250 mcg/mL. The fraction bound decreased as blood concentration increased.

Carbamazepine and phenytoin do not alter the binding of immediate-release topiramate. Sodium valproate, at 500 mcg/mL (a concentration 5 to 10 times higher than considered therapeutic for valproate) decreased the protein binding of immediate-release topiramate from 23% to 13%. Immediate-release topiramate does not influence the binding of sodium valproate.

Metabolism and Excretion

Topiramate is not extensively metabolized and is primarily eliminated unchanged in the urine (approximately 70% of an administered dose). Six metabolites have been identified in humans, none of which constitutes more than 5% of an administered dose. The metabolites are formed via hydroxylation, hydrolysis, and glucuronidation. There is evidence of renal tubular reabsorption of topiramate. In rats, given probenecid to inhibit tubular reabsorption, along with topiramate, a significant increase in renal clearance of topiramate was observed. This interaction has not been evaluated in humans. Overall, oral plasma clearance (CL/F) is approximately 20 mL/min to 30 mL/min in adults following oral administration. The mean effective half-life of QUDEXY XR is approximately 56 hours. Steady-state is reached in about 5 days after QUDEXY XR dosing in subjects with normal renal function.

Specific Populations

Renal Impairment

The clearance of topiramate was reduced by 42% in subjects with moderate renal impairment (creatinine clearance 30 to 69 mL/min/1.73 m^2) and by 54% in subjects with severe renal impairment (creatinine clearance less than 30 mL/min/1.73 m^2) compared to subjects with normal renal function (creatinine clearance greater than 70 mL/min/1.73 m^2) [see Dosage and Administration (2.4, 2.6)] .

Hemodialysis

Topiramate is cleared by hemodialysis. Using a high-efficiency, counter flow, single pass-dialysate hemodialysis procedure, topiramate dialysis clearance was 120 mL/min with blood flow through the dialyzer at 400 mL/min. This high clearance (compared to 20 mL/min to 30 mL/min total oral clearance in healthy adults) will remove a clinically significant amount of topiramate from the patient over the hemodialysis treatment period [see Dosage and Administration (2.5)and Use in Specific Populations (8.7)] .

Hepatic Impairment

Plasma clearance of topiramate decreased a mean of 26% in patients with moderate to severe hepatic impairment.

Age, Gender and Race

The pharmacokinetics of topiramate in elderly subjects (65 to 85 years of age, N=16) were evaluated in a controlled clinical study. The elderly subject population had reduced renal function (creatinine clearance [-20%]) compared to young adults. Following a single oral 100 mg dose, maximum plasma concentration for elderly and young adults was achieved at approximately 1 to 2 hours. Reflecting the primary renal elimination of topiramate, topiramate plasma and renal clearance were reduced 21% and 19%, respectively, in elderly subjects, compared to young adults. Similarly, topiramate half-life was longer (13%) in the elderly. Reduced topiramate clearance resulted in slightly higher maximum plasma concentration (23%) and AUC (25%) in elderly subjects than observed in young adults. Topiramate clearance is decreased in the elderly only to the extent that renal function is reduced [see Dosage and Administration (2.3), Use in Specific Populations (8.5)] .

Clearance of topiramate in adults was not affected by gender or race.

Pediatric Pharmacokinetics

Pharmacokinetics of immediate-release topiramate were evaluated in patients age 2 years to less than 16 years. Patients received either no or a combination of other antiepileptic drugs. A population pharmacokinetic model was developed on the basis of pharmacokinetic data from relevant topiramate clinical studies. This dataset contained data from 1,217 subjects including 258 pediatric patients age 2 years to less than 16 years (95 pediatric patients less than 10 years of age).

Pediatric patients on adjunctive treatment exhibited a higher oral clearance (L/h) of topiramate compared to patients on monotherapy, presumably because of increased clearance from concomitant enzyme-inducing antiepileptic drugs. In comparison, topiramate clearance per kg is greater in pediatric patients than in adults and in young pediatric patients (down to 2 years) than in older pediatric patients. Consequently, the plasma drug concentration for the same mg/kg/day dose would be lower in pediatric patients compared to adults and also in younger pediatric patients compared to older pediatric patients. Clearance was independent of dose.

As in adults, hepatic enzyme-inducing antiepileptic drugs decrease the steady state plasma concentrations of topiramate.

Pediatric Patients with Obesity

A population PK analysis of topiramate was conducted in 129 children <21 years of age with and without obesity to evaluate the potential impact of obesity on plasma topiramate exposures. Obesity was defined as BMI ≥95th percentile for age and sex based on CDC-recommended BMI-for-age growth charts for males and females. Using the currently recommended dosing regimens, children with obesity are likely to have median values of average concentration at steady-state and trough concentration at steady-state that are up to 20% lower and 19% lower, respectively, compared to children without obesity. Dosage adjustment according to obesity status is not necessary..

Drug Interactions

In vitros tudies indicate that topiramate does not inhibit CYP1A2, CYP2A6, CYP2B6, CYP2C9, CYP2D6, CYP2E1, or CYP3A4/5 isozymes. In vitrostudies indicate that topiramate is a mild inhibitor of CYP2C19 and a mild inducer of CYP3A4.

Antiepileptic Drugs

Potential interactions between immediate-release topiramate and standard AEDs were assessed in controlled clinical pharmacokinetic studies in patients with epilepsy. The effects of these interactions on mean plasma AUCs are summarized in Table 12. Interaction of QUDEXY XR and standard AEDs is not expected to differ from the experience with immediate-release topiramate products.

In Table 12, the second column (AED concentration) describes what happens to the concentration of the co‑administered AED listed in the first column when topiramate was added. The third column (topiramate concentration) describes how the co‑administration of a drug listed in the first column modifies the concentration of topiramate when compared to topiramate given alone.

Table 12: Summary of AED Interactions with Topiramate
AED; Co‑administered | AED; Concentration | Topiramate Concentration
Phenytoin | NC or 25% increase [Plasma concentration increased 25% in some patients, generally those on a twice a day dosing regimen of phenytoin] | 48% decrease
Carbamazepine (CBZ) | NC | 40% decrease
CBZ epoxide [Is not administered, but is an active metabolite of carbamazepine] | NC | NE
Valproic acid | 11% decrease | 14% decrease
Phenobarbital | NC | NE
Primidone | NC | NE
Lamotrigine | NC at TPM doses up to 400 mg per day | 13% decrease

NC=Less than 10% change in plasma concentration

AED=Antiepileptic drug

NE=Not evaluated

TPM=topiramate

Oral Contraceptives

In a pharmacokinetic interaction study in healthy volunteers with a concomitantly administered combination oral contraceptive product containing 1 mg norethindrone (NET) plus 35 mcg ethinyl estradiol (EE), topiramate, given in the absence of other medications at doses of 50 to 200 mg per day, was not associated with statistically significant changes in mean exposure (AUC) to either component of the oral contraceptive. In another study, exposure to EE was statistically significantly decreased at doses of 200, 400, and 800 mg per day (18%, 21%, and 30%, respectively) when given as adjunctive therapy in patients taking valproic acid. In both studies, topiramate (50 mg per day to 800 mg per day) did not significantly affect exposure to NET and there was no significant dose-dependent change in EE exposure for doses of 50 to 200 mg per day. The clinical significance of the changes observed is not known [see Drug Interactions (7.4)] .

Digoxin

In a single-dose study, serum digoxin AUC was decreased by 12% with concomitant topiramate administration. The clinical relevance of this observation has not been established.

Hydrochlorothiazide

A drug interaction study conducted in healthy volunteers evaluated the steady-state pharmacokinetics of hydrochlorothiazide (HCTZ) (25 mg every 24 hours) and topiramate (96 mg every 12 hours) when administered alone and concomitantly. The results of this study indicate that topiramate Cmaxincreased by 27% and AUC increased by 29% when HCTZ was added to topiramate. The clinical significance of this change is unknown. The steady-state pharmacokinetics of HCTZ were not significantly influenced by the concomitant administration of topiramate. Clinical laboratory results indicated decreases in serum potassium after topiramate or HCTZ administration, which were greater when HCTZ and topiramate were administered in combination.

Metformin

A drug interaction study conducted in healthy volunteers evaluated the steady-state pharmacokinetics of metformin (500 mg every 12 hours) and topiramate in plasma when metformin was given alone and when metformin and topiramate (100 mg every 12 hours) were given simultaneously. The results of this study indicated that the mean metformin Cmaxand AUC0–12hincreased by 18% and 25%, respectively, when topiramate was added. Topiramate did not affect metformin Tmax. The clinical significance of the effect of topiramate on metformin pharmacokinetics is not known. Oral plasma clearance of topiramate appears to be reduced when administered with metformin. The clinical significance of the effect of metformin on topiramate pharmacokinetics is unclear.

Pioglitazone

A drug interaction study conducted in healthy volunteers evaluated the steady-state pharmacokinetics of topiramate and pioglitazone when administered alone and concomitantly. A 15% decrease in the AUCτ,ssof pioglitazone with no alteration in Cmax,sswas observed. This finding was not statistically significant. In addition, a 13% and 16% decrease in Cmax,ssand AUCτ,ssrespectively, of the active hydroxy-metabolite was noted as well as a 60% decrease in Cmax,ssand AUCτ,ssof the active keto-metabolite. The clinical significance of these findings is not known.

Glyburide

A drug-drug interaction study conducted in patients with type 2 diabetes evaluated the steady-state pharmacokinetics of glyburide (5 mg per day) alone and concomitantly with topiramate (150 mg per day). There was a 22% decrease in Cmaxand a 25% reduction in AUC24for glyburide during topiramate administration. Systemic exposure (AUC) of the active metabolites, 4- trans-hydroxy glyburide (M1) and 3- cis-hydroxyglyburide (M2), was also reduced by 13% and 15% and Cmaxwas reduced by 18% and 25%, respectively. The steady-state pharmacokinetics of topiramate were unaffected by concomitant administration of glyburide.

Lithium

In patients, the pharmacokinetics of lithium were unaffected during treatment with topiramate at doses of 200 mg per day; however, there was an observed increase in systemic exposure of lithium (27% for Cmaxand 26% for AUC) following topiramate doses up to 600 mg per day [see Drug Interactions (7.7)] .

Haloperidol

The pharmacokinetics of a single dose of haloperidol (5 mg) were not affected following multiple dosing of topiramate (100 mg every 12 hr) in 13 healthy adults (6 males, 7 females).

Amitriptyline

There was a 12% increase in AUC and Cmaxfor amitriptyline (25 mg per day) in 18 healthy subjects (9 males, 9 females) receiving 200 mg per day of topiramate.

Sumatriptan

Multiple dosing of topiramate (100 mg every 12 hours) in 24 healthy volunteers (14 males, 10 females) did not affect the pharmacokinetics of single-dose sumatriptan either orally (100 mg) or subcutaneously (6 mg).

Risperidone

When administered concomitantly with topiramate at escalating doses of 100, 250, and 400 mg per day, there was a reduction in risperidone systemic exposure (16% and 33% for steady-state AUC at the 250 and 400 mg per day doses of topiramate). No alterations of 9-hydroxyrisperidone levels were observed. Coadministration of topiramate 400 mg per day with risperidone resulted in a 14% increase in Cmaxand a 12% increase in AUC12of topiramate. There were no clinically significant changes in the systemic exposure of risperidone plus 9- hydroxyrisperidone or of topiramate; therefore, this interaction is not likely to be of clinical significance.

Propranolol

Multiple dosing of topiramate (200 mg per day) in 34 healthy volunteers (17 males, 17 females) did not affect the pharmacokinetics of propranolol following daily 160 mg doses. Propranolol doses of 160 mg per day in 39 volunteers (27 males, 12 females) had no effect on the exposure to topiramate, at a dose of 200 mg per day of topiramate.

Dihydroergotamine

Multiple dosing of topiramate (200 mg per day) in 24 healthy volunteers (12 males, 12 females) did not affect the pharmacokinetics of a 1 mg subcutaneous dose of dihydroergotamine. Similarly, a 1 mg subcutaneous dose of dihydroergotamine did not affect the pharmacokinetics of a 200 mg per day dose of topiramate in the same study.

Diltiazem

Coadministration of diltiazem (240 mg Cardizem CD®) with topiramate (150 mg per day) resulted in a 10% decrease in Cmaxand 25% decrease in diltiazem AUC, a 27% decrease in Cmaxand an 18% decrease in des-acetyl diltiazem AUC, and no effect on N-desmethyl diltiazem. Co-administration of topiramate with diltiazem resulted in a 16% increase in Cmaxand a 19% increase in AUC12of topiramate.

Venlafaxine

Multiple dosing of topiramate (150 mg per day) in healthy volunteers did not affect the pharmacokinetics of venlafaxine or O-desmethyl venlafaxine. Multiple dosing of venlafaxine (150 mg) did not affect the pharmacokinetics of topiramate.

12.6 Relative Bioavailability of QUDEXY XR Compared to Immediate-Release Topiramate in Healthy Volunteers

QUDEXY XR, taken once daily, provides similar steady-state topiramate concentrations to immediate-release topiramate taken every 12 hours, when administered at the same total daily dose. In a healthy volunteer, multiple-dose crossover study, the 90% CI for the ratios of AUC0–24, Cmaxand Cmin, as well as partial AUC (the area under the concentration-time curve from time 0 to time p (post dose)) for multiple time points were within the 80% to 125% bioequivalence limits, indicating no clinically significant difference between the two formulations. In addition, the 90% CI for the ratios of topiramate plasma concentration at each of multiple time points over 24 hours for the two formulations were within the 80% to 125% bioequivalence limits, except for the initial time points before 3 hours and at 8 hours post-dose, which is not expected to have a significant clinical impact.

The effects of switching between QUDEXY XR and immediate-release topiramate were also evaluated in the same multiple-dose, crossover, comparative bioavailability study. In healthy subjects switched from immediate-release topiramate given every 12 hours to QUDEXY XR given once daily, similar concentrations were maintained immediately after the formulation switch. On the first day following the switch, there were no significant differences in AUC0–24, Cmax, and Cmin, as the 90% CI for the ratios were contained within the 80% to 125% equivalence limits.

13 NON-CLINICAL TOXICOLOGY

13.1 Carcinogenesis, Mutagenesis, Impairment of Fertility

Carcinogenesis

An increase in urinary bladder tumors was observed in mice given topiramate (0, 20, 75, and 300 mg/kg/day) in the diet for 21 months. An increase in the incidence of bladder tumors in males and females receiving 300 mg/kg/day was primarily due to the increased occurrence of a smooth muscle tumor considered histomorphologically unique to mice. The higher of the doses not associated with an increase in tumors (75 mg/kg/day) is equivalent to the maximum recommended human dose (MRHD) for epilepsy (400 mg) and approximately 4 times the MRHD for migraine (100 mg) on a mg/m^2basis. The relevance of this finding to human carcinogenic risk is uncertain.

No evidence of carcinogenicity was seen in rats following oral administration of topiramate for 2 years at doses up to 120 mg/kg/day (approximately 3 times the MRHD for epilepsy and 12 times the MRHD for migraine on a mg/m^2basis).

Mutagenesis

Topiramate did not demonstrate genotoxic potential when tested in a battery of in vitroand in vivoassays. Topiramate was not mutagenic in the Ames test or the in vitromouse lymphoma assay; it did not increase unscheduled DNA synthesis in rat hepatocytes in vitro; and it did not increase chromosomal aberrations in human lymphocytes in vitroor in rat bone marrow in vivo.

Impairment of Fertility

No adverse effects on male or female fertility were observed in rats administered topiramate orally at doses up to 100 mg/kg/day (2.5 times the MRHD for epilepsy and 10 times the MRHD for migraine on a mg/m^2basis) prior to and during mating and early pregnancy.

14 CLINICAL STUDIES

14.1 Extended-Release: Bridging Study to Demonstrate Pharmacokinetic Equivalence between Extended-Release (QUDEXY XR) and Immediate-Release Topiramate Formulations

Although a controlled clinical trial was performed (Study 14) [see Clinical Studies (14.4)] , the basis for approval of the extended-release formulation (QUDEXY XR) included the studies described below using an immediate-release formulation [see Clinical Studies (14.2, 14.3, 14.5)] and the demonstration of the pharmacokinetic equivalence of QUDEXY XR to immediate-release topiramate through the analysis of concentrations and cumulative AUCs at multiple time points [see Clinical Pharmacology (12.6)] .

14.2 Monotherapy Epilepsy

Patients with Partial-Onset or Primary Generalized Tonic-Clonic Seizures

Adults and Pediatric Patients 10 Years of Age and Older

The effectiveness of topiramate as initial monotherapy in adults and pediatric patients 10 years of age and older with partial-onset or primary generalized tonic-clonic seizures was established in a multicenter, randomized, double-blind, dose-controlled, parallel-group trial (Study 1).

Study 1 was conducted in 487 patients diagnosed with epilepsy (6 to 83 years of age) who had 1 or 2 well-documented seizures during the 3-month retrospective baseline phase who then entered the study and received topiramate 25 mg/day for 7 days in an open-label fashion. Forty-nine percent of subjects had no prior AED treatment and 17% had a diagnosis of epilepsy for greater than 24 months. Any AED therapy used for temporary or emergency purposes was discontinued prior to randomization. In the double-blind phase, 470 patients were randomized to titrate up to 50 mg/day or 400 mg/day of topiramate. If the target dose could not be achieved, patients were maintained on the maximum tolerated dose. Fifty-eight percent of patients achieved the maximal dose of 400 mg/day for >2 weeks, and patients who did not tolerate 150 mg/day were discontinued.

The primary efficacy assessment was a between-group comparison of time to first seizure during the double-blind phase. Comparison of the Kaplan-Meier survival curves of time to first seizure favored the topiramate 400 mg/day group over the topiramate 50 mg/day group (Figure 1). The treatment effects with respect to time to first seizure were consistent across various patient subgroups defined by age, sex, geographic region, baseline body weight, baseline seizure type, time since diagnosis, and baseline AED use.

Figure 1: Kaplan-Meier Estimates of Cumulative Rates for Time to First Seizure in Study 1

Pediatric Patients 2 to 9 Years of Age

The conclusion that topiramate is effective as initial monotherapy in pediatric patients 2 to 9 years of age with partial-onset or primary generalized tonic-clonic seizures was based on a pharmacometric bridging approach using data from the controlled epilepsy trials conducted with immediate-release topiramate described in labeling. This approach consisted of first showing a similar exposure-response relationship between pediatric patients down to 2 years of age and adults when immediate-release topiramate was given as adjunctive therapy. Similarity of exposure-response was also demonstrated in pediatric patients 6 to less than 16 years of age and adults when topiramate was given as initial monotherapy. Specific dosing in pediatric patients 2 to 9 years of age was derived from simulations utilizing plasma exposure ranges observed in pediatric and adult patients treated with immediate-release topiramate initial monotherapy [see Dosage and Administration (2.1)] .

14.3 Adjunctive Therapy Epilepsy

Adult Patients with Partial-Onset Seizures

The effectiveness of topiramate as an adjunctive treatment for adults with partial-onset seizures was established in six multicenter, randomized, double-blind, placebo-controlled trials (Studies 2, 3, 4, 5, 6, and 7), two comparing several dosages of topiramate and placebo and four comparing a single dosage with placebo, in patients with a history of partial-onset seizures, with or without secondarily generalized seizures.

Patients in these studies were permitted a maximum of two antiepileptic drugs (AEDs) in addition to topiramate tablets or placebo. In each study, patients were stabilized on optimum dosages of their concomitant AEDs during baseline phase lasting between 4 and 12 weeks. Patients who experienced a pre-specified minimum number of partial onset seizures, with or without secondary generalization, during the baseline phase (12 seizures for 12-week baseline, 8 for 8-week baseline or 3 for 4-week baseline) were randomly assigned to placebo or a specified dose of topiramate tablets in addition to their other AEDs.

Following randomization, patients began the double-blind phase of treatment. In five of the six studies, patients received active drug beginning at 100 mg per day; the dose was then increased by 100 mg or 200 mg/day increments weekly or every other week until the assigned dose was reached, unless intolerance prevented increases. In Study 7, the 25 or 50 mg/day initial doses of topiramate were followed by respective weekly increments of 25 or 50 mg/day until the target dose of 200 mg/day was reached. After titration, patients entered a 4, 8 or 12-week stabilization period. The numbers of patients randomized to each dose and the actual mean and median doses in the stabilization period are shown in Table 13.

Pediatric Patients 2 to 16 Years of Age with Partial-Onset Seizures

The effectiveness of topiramate as an adjunctive treatment for pediatric patients 2 to 16 years of age with partial-onset seizures was established in a multicenter, randomized, double-blind, placebo-controlled trial (Study 8), comparing topiramate and placebo in patients with a history of partial-onset seizures, with or without secondarily generalized seizures (see Table 14).

Patients in this study were permitted a maximum of two antiepileptic drugs (AEDs) in addition to topiramate tablets or placebo. In Study 8, patients were stabilized on optimum dosages of their concomitant AEDs during an 8-week baseline phase. Patients who experienced at least six partial-onset seizures, with or without secondarily generalized seizures, during the baseline phase were randomly assigned to placebo or topiramate tablets in addition to their other AEDs.

Following randomization, patients began the double-blind phase of treatment. Patients received active drug beginning at 25 or 50 mg/day; the dose was then increased by 25 mg to 150 mg/day increments every other week until the assigned dosage of 125, 175, 225, or 400 mg/day based on patients' weight to approximate a dosage of 6 mg/kg/day was reached, unless intolerance prevented increases. After titration, patients entered an 8-week stabilization period.

Patients with Primary Generalized Tonic-Clonic Seizures

The effectiveness of topiramate as an adjunctive treatment for primary generalized tonic-clonic seizures in patients 2 years of age and older was established in a multicenter, randomized, double-blind, placebo-controlled trial (Study 9), comparing a single dosage of topiramate and placebo (see Table 14).

Patients in Study 9 were permitted a maximum of two antiepileptic drugs (AEDs) in addition to topiramate or placebo. Patients were stabilized on optimum dosages of their concomitant AEDs during an 8-week baseline phase. Patients who experienced at least three primary generalized tonic-clonic seizures during the baseline phase were randomly assigned to placebo or topiramate in addition to their other AEDs.

Following randomization, patients began the double-blind phase of treatment. Patients received active drug beginning at 50 mg/day for four weeks; the dose was then increased by 50 mg to 150 mg/day increments every other week until the assigned dose of 175, 225, or 400 mg/day based on patients' body weight to approximate a dosage of 6 mg/kg/day was reached, unless intolerance prevented increases. After titration, patients entered a 12-week stabilization period.

Patients with Lennox-Gastaut Syndrome

The effectiveness of topiramate as an adjunctive treatment for seizures associated with Lennox-Gastaut syndrome in patients 2 years of age and older was established in a multicenter, randomized, double-blind, placebo-controlled trial (Study 10) comparing a single dosage of topiramate with placebo (see Table 14).

Patients in Study 10 were permitted a maximum of two antiepileptic drugs (AEDs) in addition to topiramate or placebo. Patients who were experiencing at least 60 seizures per month before study entry were stabilized on optimum dosages of their concomitant AEDs during a 4-week baseline phase. Following baseline, patients were randomly assigned to placebo or topiramate in addition to their other AEDs. Active drug was titrated beginning at 1 mg/kg/day for a week; the dose was then increased to 3 mg/kg/day for one week, then to 6 mg/kg/day. After titration, patients entered an 8-week stabilization period. The primary measures of effectiveness were the percent reduction in drop attacks and a parental global rating of seizure severity.

Table 13: Immediate-Release Topiramate Dose Summary During the Stabilization Periods of Each of Six Double-Blind, Placebo-Controlled, Adjunctive Trials in Adults with Partial-Onset Seizures [Dose-response studies were not conducted for other indications or pediatric partial-onset seizures]
 |  |  | Target Topiramate Dosage (mg/day)
Study | Stabilization Dose | Placebo [Placebo dosages are given as the number of tablets. Placebo target dosages were as follows: Study 4 (4 tablets/day); Studies 2 and 5 (6 tablets/day); Studies 6 and 7 (8 tablets/day); Study 3 (10 tablets/day)] | 200 | 400 | 600 | 800 | 1,000
2 | N | 42 | 42 | 40 | 41 | -- | --
2 | Mean Dose | 5.9 | 200 | 390 | 556 | -- | --
2 | Median Dose | 6.0 | 200 | 400 | 600 | -- | --
3 | N | 44 | -- | -- | 40 | 45 | 40
3 | Mean Dose | 9.7 | -- | -- | 544 | 739 | 796
3 | Median Dose | 10.0 | -- | -- | 600 | 800 | 1,000
4 | N | 23 | -- | 19 | -- | -- | --
4 | Mean Dose | 3.8 | -- | 395 | -- | -- | --
4 | Median Dose | 4.0 | -- | 400 | -- | -- | --
5 | N | 30 | -- | -- | 28 | -- | --
5 | Mean Dose | 5.7 | -- | -- | 522 | -- | --
5 | Median Dose | 6.0 | -- | -- | 600 | -- | --
6 | N | 28 | -- | -- | -- | 25 | --
6 | Mean Dose | 7.9 | -- | -- | -- | 568 | --
6 | Median Dose | 8 | -- | -- | -- | 600 | --
7 | N | 90 | 157 | -- | -- | -- | --
7 | Mean Dose | 8 | 200 | -- | -- | -- | --
7 | Median Dose | 8 | 200 | -- | -- | -- | --

In all adjunctive topiramate trials, the reduction in seizure rate from baseline during the entire double-blind phase was measured. The median percent reductions in seizure rates and the responder rates (fraction of patients with at least a 50% reduction) by treatment group for each study are shown below in Table 14. As described above, a global improvement in seizure severity was also assessed in the Lennox-Gastaut trial.

Table 14: Efficacy Results in Double-Blind, Placebo-Controlled, Adjunctive Epilepsy Trials
 |  |  | Target Topiramate Dosage (mg per day)
Study # | # | Placebo | 200 | 400 | 600 | 800 | 1,000 | ≈6 mg/kg/day [For Studies 8 and 9, specified target dosages (less than 9.3 mg/kg/day) were assigned based on subject's weight to approximate a dosage of 6 mg/kg/day; these dosages corresponded to mg per day dosages of 125 mg per day, 175 mg per day, 225 mg per day, and 400 mg per day]
Partial-Onset Seizures Studies in Adults
2 | N | 45 | 45 | 45 | 46 | -- | -- | --
2 | Median % Reduction | 12 | 27 [p=0.080;] | 48 [p ≤ 0.010;] | 45 [p ≤ 0.001;] | -- | -- | --
2 | % Responders | 18 | 24 | 44 [p ≤ 0.050;] | 46 | -- | -- | --
3 | N | 47 | -- | -- | 48 | 48 | 47 | --
3 | Median % Reduction | 2 | -- | -- | 41 | 41 | 36
3 | % Responders | 9 | -- | -- | 40 | 41 | 36
4 | N | 24 | -- | 23 | -- | -- | -- | --
4 | Median % Reduction | 1 | -- | 41 [p=0.065;] | -- | -- | -- | --
4 | % Responders | 8 | -- | 35 | -- | -- | -- | --
5 | N | 30 | -- | -- | 30 | -- | -- | --
5 | Median % Reduction | -12 | -- | -- | 46 [p ≤0.005;] | -- | -- | --
5 | % Responders | 10 | -- | -- | 47 | -- | -- | --
6 | N | 28 | -- | -- | -- | 28 | -- | --
6 | Median % Reduction | -21 | -- | -- | -- | 24 | -- | --
6 | % Responders | 0 | -- | -- | -- | 43 | -- | --
7 | N | 91 | 168 | -- | -- | -- | -- | --
7 | Median % Reduction | 20 | 44 | -- | -- | -- | -- | --
7 | % Responders | 24 | 45
Partial-Onset Seizures Studies in Pediatric Patients
8 | N | 45 | -- | -- | -- | -- | -- | 41
8 | Median % Reduction | 11 | -- | -- | -- | -- | -- | 33
8 | % Responders | 20 | -- | -- | -- | -- | -- | 39
Primary Generalized Tonic-Clonic [Median % reduction and % responders are reported for PGTC seizures]
9 | N | 40 | -- | -- | -- | -- | -- | 39
9 | Median % Reduction | 9 | -- | -- | -- | -- | -- | 57
9 | % Responders | 20 | -- | -- | -- | -- | -- | 56
Lennox-Gastaut Syndrome [Median % reduction and % responders for drop attacks, i.e., tonic or atonic seizures]
10 | N | 49 | -- | -- | -- | -- | -- | 46
10 | Median % Reduction | -5 | -- | -- | -- | -- | -- | 15
10 | % Responders | 14 |  |  |  |  |  | 28 [p=0.071]
10 | Improvement in Seizure Severity [Percent of subjects who were minimally, much, or very much improved from baseline.] | 28 |  |  |  |  |  | 52
Comparisons with placebo:

Subset analyses of the antiepileptic efficacy of topiramate tablets in these studies showed no differences as a function of gender, race, age, baseline seizure rate, or concomitant AED.

In clinical trials for epilepsy, daily dosages were decreased in weekly intervals by 50 to 100 mg/day in adults and over a 2- to 8-week period in pediatric patients; transition was permitted to a new antiepileptic regimen when clinically indicated.

14.4 Extended-Release: Adjunctive Therapy in Adult Patients with Partial-Onset Seizures with QUDEXY XR

The effectiveness of QUDEXY XR as an adjunctive treatment for adults (18 to 75 years of age) was evaluated in a randomized, international, multi-center, double-blind, parallel-group, placebo-controlled trial in patients with a history of partial-onset seizures, with or without secondary generalization (Study 14).

Patients with partial-onset seizures on a stable dose of 1 to 3 AEDs entered into an 8-week baseline period. Patients who experienced at least 8 partial onset seizures, with or without secondary generalization, and no more than 21 consecutive seizure free days during the 8-week baseline phase were randomly assigned to placebo or QUDEXY XR administered once daily in addition to their concomitant AEDs. Following randomization, 249 patients began the double-blind treatment phase, which consisted of an initial 3-week titration period followed by an 8-week maintenance period. During the titration period, patients received QUDEXY XR or placebo beginning at 50 mg once daily; the dose was increased at weekly intervals by 50 mg once daily, or the placebo equivalent, until a final dose of 200 mg once daily was achieved. Patients then entered the maintenance period at the assigned dose of 200 mg once daily, or its placebo equivalent.

The percent reduction in the frequency of partial-onset seizure, baseline period compared to the treatment phase, was the primary endpoint. Data was analyzed by the Wilcoxon rank-sum test, with the criteria of statistical significance of p<0.05. The results of the analysis are presented in Table 15. The median percent reduction in seizure rate was 39.5% in patients taking QUDEXY XR (N=124) and 21.7% in patients taking placebo (N=125). This difference was statistically significant.

Table 15: Percent Reduction From Baseline in Partial-Onset Seizure Frequency During 11-week Treatment Period in Study 14
Study End Point | QUDEXY XR (N=124) | Placebo (N=125)
Median Percent Reduction from Baseline [Statistically Significant by the Wilcoxon rank-sum test] | 39.5% | 21.7%

Figure 2 shows the change from baseline during titration plus maintenance (11 weeks) in partial-onset seizure frequency by category for patients treated with QUDEXY XR and placebo. Patients in whom the seizure frequency increased are shown as "worse." Patients in whom the seizure frequency decreased are shown in four categories of reduction in seizure frequency.

Figure 2: Proportion of Patients by Category of Seizure Response to QUDEXY XR and Placebo

14.5 Preventive Treatment of Migraine

Adult Patients

The results of 2 multicenter, randomized, double-blind, placebo-controlled, parallel-group clinical trials conducted in the US (Study 11) or the US and Canada (Study 12) established the effectiveness of immediate-release topiramate in the preventive treatment of migraine. The design of both trials was identical, enrolling patients with a history of migraine, with or without aura, for at least 6 months, according to the International Headache Society (IHS) diagnostic criteria. Patients with a history of cluster headaches or basilar, ophthalmoplegic, hemiplegic, or transformed migraine headaches were excluded from the trials. Patients were required to have completed up to a 2-week washout of any prior migraine preventive medications before starting the baseline phase.

Patients who experienced 3 to 12 migraine headaches over the 4 weeks in the baseline phase were randomized to either topiramate 50 mg/day, 100 mg/day, 200 mg/day (twice the recommended daily dosage for the preventive treatment of migraine), or placebo and treated for a total of 26 weeks (8-week titration period and 18-week maintenance period). Treatment was initiated at 25 mg/day for one week, and then the daily dosage was increased by 25 mg increments each week until reaching the assigned target dose or maximum tolerated dose (administered twice daily).

Effectiveness of treatment was assessed by the reduction in migraine headache frequency, as measured by the change in 4-week migraine rate (according to migraines classified by IHS criteria) from the baseline phase to double-blind treatment period in each immediate-release topiramate treatment group compared to placebo in the Intent-To-Treat (ITT) population.

In Study 11, a total of 469 patients (416 females, 53 males), ranging in age from 13 to 70 years, were randomized and provided efficacy data. Two hundred sixty-five patients completed the entire 26-week double-blind phase. The median average daily dosages were 48 mg/day, 88 mg/day, and 132 mg/day in the target dose groups of topiramate 50, 100, and 200 mg/day, respectively.

The mean migraine headache frequency rate at baseline was approximately 5.5 migraine headaches per 28 days and was similar across treatment groups. The change in the mean 4-week migraine headache frequency from baseline to the double-blind phase was -1.3, -2.1, and -2.2 in the immediate-release topiramate 50, 100, and 200 mg/day groups, respectively, versus -0.8 in the placebo group (see Figure 3). The treatment differences between the immediate-release topiramate 100 and 200 mg/day groups versus placebo were similar and statistically significant (p<0.001 for both comparisons).

In Study 12, a total of 468 patients (406 females, 62 males), ranging in age from 12 to 65 years, were randomized and provided efficacy data. Two hundred fifty-five patients completed the entire 26-week double-blind phase. The median average daily dosages were 47 mg/day, 86 mg/day, and 150 mg/day in the target dose groups of immediate-release topiramate 50, 100, and 200 mg/day, respectively.

The mean migraine headache frequency rate at baseline was approximately 5.5 migraine headaches per 28 days and was similar across treatment groups. The change in the mean 4-week migraine headache period frequency from baseline to the double-blind phase was -1.4, -2.1, and -2.4 in the immediate-release topiramate 50, 100, and 200 mg/day groups, respectively, versus -1.1 in the placebo group (see Figure 3). The differences between the immediate-release topiramate 100 and 200 mg/day groups versus placebo were similar and statistically significant (p=0.008 and p <0.001, respectively).

In both studies, there were no apparent differences in treatment effect within age or gender subgroups. Because most patients were Caucasian, there were insufficient numbers of patients from different races to make a meaningful comparison of race.

For patients withdrawing from immediate-release topiramate, daily dosages were decreased in weekly intervals by 25 to 50 mg/day.

Figure 3: Reduction in 4-Week Migraine Headache Frequency(Studies 11 and 12 for Adults and Adolescents)

Pediatric Patients 12 to 17 Years of Age

The effectiveness of immediate-release topiramate for the preventive treatment of migraine in pediatric patients 12 to 17 years of age was established in a multicenter, randomized, double-blind, parallel-group trial (Study 13). The study enrolled 103 patients (40 male, 63 female) 12 to 17 years of age with episodic migraine headaches with or without aura. Patient selection was based on IHS criteria for migraines (using proposed revisions to the 1988 IHS pediatric migraine criteria [IHS-R criteria]).

Patients who experienced 3 to 12 migraine attacks (according to migraines classified by patient reported diaries) and ≤14 headache days (migraine and non-migraine) during the 4-week prospective baseline period were randomized to either immediate-release topiramate 50 mg/day, 100 mg/day, or placebo and treated for a total of 16 weeks (4-week titration period followed by a 12-week maintenance period). Treatment was initiated at 25 mg/day for one week, and then the daily dosage was increased by 25 mg increments each week until reaching the assigned target dose or maximum tolerated dose (administered twice daily). Approximately 80% or more patients in each treatment group completed the study. The median average daily dosages were 45 and 79 mg/day in the target dose groups of immediate-release topiramate 50 and 100 mg/day, respectively.

Effectiveness of treatment was assessed by comparing each immediate-release topiramate treatment group to placebo (ITT population) for the percent reduction from baseline to the last 12 weeks of the double-blind phase in the monthly migraine attack rate (primary endpoint). The percent reduction from baseline to the last 12 weeks of the double-blind phase in average monthly migraine attack rate is shown in Table 16. The 100 mg immediate-release topiramate dose produced a statistically significant treatment difference relative to placebo of 28% reduction from baseline in the monthly migraine attack rate.

The mean reduction from baseline to the last 12 weeks of the double-blind phase in average monthly attack rate, a key secondary efficacy endpoint in Study 13 (and the primary efficacy endpoint in Studies 11 and 12, of adults) was 3.0 for 100 mg immediate-release topiramate dose and 1.7 for placebo. This 1.3 treatment difference in mean reduction from baseline of monthly migraine rate was statistically significant (p = 0.0087).

Table 16: Percent Reduction from Baseline to the Last 12 Weeks of Double-Blind Phase in Average Monthly Attack Rate: Study 13 (Intent-to-Treat Analysis Set)
Category | Placebo (N=33) | Topiramate 50 mg/day (N=35) | Topiramate 100 mg/day (N=35)
Baseline
Median | 3.6 | 4.0 | 4.0
Last 12 Weeks of Double-Blind Phase
Median | 2.3 | 2.3 | 1.0
Percent Reduction (%)
Median | 44.4 | 44.6 | 72.2
P-value versus Placebo [P-values (two-sided) for comparisons relative to placebo are generated by applying an ANCOVA model on ranks that includes subject's stratified age at baseline, treatment group, and analysis center as factors and monthly migraine attack rate during baseline period as a covariate.] , [P-values for the dose groups are the adjusted p-value according to the Hochberg multiple comparison procedure.] |  | 0.7975 | 0.0164 [Indicates p-value is < 0.05 (two-sided).]

16 HOW SUPPLIED/STORAGE AND HANDLING

16.1 How Supplied

QUDEXY®XR (topiramate) extended-release capsules contain beads of topiramate in a capsule and are available in the following strengths and colors:

25 mg: light pink and grey capsules, printed with "UPSHER-SMITH" on the cap in black ink and "25 mg" on the body in black ink. 25 mg capsules are supplied in the following package configurations:

- Bottles of 30 with desiccant and a child-resistant closure, NDC 0245-1071-30
- Bottles of 90 with desiccant and a child-resistant closure, NDC 0245-1071-90

50 mg: golden yellow and grey capsules, printed with "UPSHER-SMITH" on the cap in black ink and "50 mg" on the body in black ink. 50 mg capsules are supplied in the following package configurations:

- Bottles of 30 with desiccant and a child-resistant closure, NDC 0245-1072-30
- Bottles of 90 with desiccant and a child-resistant closure, NDC 0245-1072-90

100 mg: reddish brown and grey capsules, printed with "UPSHER-SMITH" on the cap in black ink and "100 mg" on the body in black ink. 100 mg capsules are supplied in the following package configurations:

- Bottles of 30 with desiccant and a child-resistant closure, NDC 0245-1074-30
- Bottles of 90 with desiccant and a child-resistant closure, NDC 0245-1074-90

150 mg: pale yellow and grey capsules, printed with "UPSHER-SMITH" on the cap in black ink and "150 mg" on the body in black ink. 150 mg capsules are supplied in the following package configurations:

- Bottles of 30 with desiccant and a child-resistant closure, NDC 0245-1075-30
- Bottles of 90 with desiccant and a child-resistant closure, NDC 0245-1075-90

200 mg: brown and grey capsules, printed with "UPSHER-SMITH" on the cap in white ink and "200 mg" on the body in black ink. 200 mg capsules are supplied in the following package configurations:

- Bottles of 30 with desiccant and a child-resistant closure, NDC 0245-1073-30
- Bottles of 90 with desiccant and a child-resistant closure, NDC 0245-1073-90

16.2 Storage and Handling

QUDEXY XR (topiramate) extended-release capsules should be stored in a tightly closed container at 20°C to 25°C (68°F to 77°F); excursions permitted to 15°C to 30°C (59°F to 86°F) [See USP Controlled Room Temperature]. Protect from moisture.

17 PATIENT COUNSELING INFORMATION

Advise patients to read the FDA-approved patient labeling (Medication Guide).

Administration Instructions

Counsel patients to swallow QUDEXY XR capsules whole or carefully open and sprinkle the entire contents on a spoonful of soft food. This drug/food mixture should be swallowed immediately and not chewed. Do not store drug/food mixture for future use [see Dosage and Administration (2.6)] .

Eye Disorders

Advise patients taking QUDEXY XR to seek immediate medical attention if they experience blurred vision, visual disturbances or periorbital pain [see Warnings and Precautions (5.1and 5.2)] .

Oligohydrosis and Hyperthermia

Closely monitor QUDEXY XR-treated patients, especially pediatric patients, for evidence of decreased sweating and increased body temperature, especially in hot weather. Counsel patients to contact their healthcare professionals immediately if they develop a high or persistent fever, or decreased sweating [see Warnings and Precautions (5.3)] .

Metabolic Acidosis

Warn patients about the potential significant risk for metabolic acidosis that may be asymptomatic and may be associated with adverse effects on kidneys (e.g., kidney stones, nephrocalcinosis), bones (e.g., osteoporosis, osteomalacia, and/or rickets in children), and growth (e.g., growth delay/retardation) in pediatric patients, and on the fetus [see Warnings and Precautions (5.4), Use in Specific Populations (8.1), (8.4)].

Suicidal Behavior and Ideation

Counsel patients, their caregivers, and families that AEDs, including QUDEXY XR, may increase the risk of suicidal thoughts and behavior and they should be advised of the need to be alert for the emergence or worsening of the signs and symptoms of depression, any unusual changes in mood or behavior or the emergence of suicidal thoughts, behavior or thoughts about self-harm. Instruct patients to immediately report behaviors of concern to their healthcare providers [see Warnings and Precautions (5.5)] .

Interference with Cognitive and Motor Performance

Warn patients about the potential for somnolence, dizziness, confusion, difficulty concentrating, visual effects, and advise patients not to drive or operate machinery until they have gained sufficient experience on QUDEXY XR to gauge whether it adversely affects their mental performance, motor performance, and/or vision [see Warnings and Precautions (5.6)] .

Even when taking QUDEXY XR, or other anticonvulsants, some patients with epilepsy will continue to have unpredictable seizures. Therefore, advise all patients taking QUDEXY XR for epilepsy to exercise appropriate caution when engaging in any activities where loss of consciousness could result in serious danger to themselves or those around them (including swimming, driving a car, climbing in high places, etc.). Some patients with refractory epilepsy will need to avoid such activities altogether. Discuss the appropriate level of caution with patients, before patients with epilepsy engage in such activities.

Fetal Toxicity

Inform pregnant women and women of childbearing potential that use of QUDEXY XR during pregnancy can cause fetal harm. QUDEXY XR increased the risk of major congenital malformations, including but not limited to cleft lip and/or cleft palate (oral clefts), which occur early in pregnancy before many women know they are pregnant. Also inform patients that infants exposed to topiramate monotherapy in uteromay be small for their gestational age. There may also be risks to the fetus from chronic metabolic acidosis with use of QUDEXY XR during pregnancy [see Warnings and Precautions (5.4), (5.7), Use in Specific Populations (8.1)] . When appropriate, counsel pregnant women and women of childbearing potential about alternative therapeutic options.

Advise women of childbearing potential who are not planning a pregnancy to use effective contraception while using QUDEXY XR, keeping in mind that there is a potential for decreased contraceptive efficacy when using estrogen-containing or progestin-only contraceptives with topiramate [see Drug Interactions (7.4)] .

Encourage pregnant women using QUDEXY XR to enroll in the North American Antiepileptic Drug (NAAED) Pregnancy Registry. The registry is collecting information about the safety of antiepileptic drugs during pregnancy [see Use in Specific Populations (8.1)] .

Decrease in Bone Mineral Density

Inform the patient or caregiver that long-term treatment with QUDEXY XR can decrease bone formation and increase bone resorption in children [see Warnings and Precautions (5.9)] .

Negative Effects on Growth (Height and Weight)

Discuss with the patient or caregiver that long-term QUDEXY XR treatment may attenuate growth as reflected by slower height increase and weight gain in pediatric patients [see Warnings and Precautions (5.10)] .

Serious Skin Reactions

Inform patients about the signs of serious skin reactions. Instruct patients to immediately inform their healthcare provider at the first appearance of skin rash [see Warnings and Precautions (5.11)].

Hyperammonemia and Encephalopathy

Warn patients about the possible development of hyperammonemia with or without encephalopathy. Although hyperammonemia may be asymptomatic, clinical symptoms of hyperammonemic encephalopathy often include acute alterations in level of consciousness and/or cognitive function with lethargy and/or vomiting. This hyperammonemia and encephalopathy can develop with topiramate treatment alone or with topiramate treatment with concomitant valproic acid (VPA).

Instruct patients to contact their physician if they develop unexplained lethargy, vomiting, or changes in mental status [see Warnings and Precautions (5.12)] .

Kidney Stones

Instruct patients, particularly those with predisposing factors, to maintain an adequate fluid intake in order to minimize the risk of kidney stone formation [see Warnings and Precautions (5.13)] .

Hypothermia

Counsel patients that QUDEXY XR can cause a reduction in body temperature, which can lead to alterations in mental status. If they note such changes, they should call their health care professional and measure their body temperature. Patients taking concomitant valproic acid should be specifically counseled on this potential adverse reaction [see Warnings and Precautions (5.14)] .

Distributed by
UPSHER-SMITH LABORATORIES, LLC
Maple Grove, MN 55369

Qudexy is a registered trademark of Upsher-Smith Laboratories, LLC. All other marks are property of their respective owners.

Drug Interactions

Antiepileptic Drugs

Potential interactions between immediate-release topiramate and standard AEDs were assessed in controlled clinical pharmacokinetic studies in patients with epilepsy. The effects of these interactions on mean plasma AUCs are summarized in Table 12. Interaction of QUDEXY XR and standard AEDs is not expected to differ from the experience with immediate-release topiramate products.

In Table 12, the second column (AED concentration) describes what happens to the concentration of the co-administered AED listed in the first column when topiramate was added. The third column (topiramate concentration) describes how the co-administration of a drug listed in the first column modifies the concentration of topiramate when compared to topiramate given alone.

MEDICATION GUIDE
QUDEXY®XR (cue-DEKS-ee ex-arr)
(topiramate) Extended-Release Capsules, for oral use

What is the most important information I should know about QUDEXY XR?

QUDEXY XR may cause eye problems.Serious eye problems include:

- any sudden decrease in vision with or without eye pain and redness,
- a blockage of fluid in the eye causing increased pressure in the eye (secondary angle closure glaucoma).

These eye problems can lead to permanent loss of vision if not treated. You should call your healthcare provider right away if you have any new eye symptoms, including any new problems with your vision.

QUDEXY XR may cause decreased sweating and increased body temperature (fever).People, especially children, should be watched for signs of decreased sweating and fever, especially in hot temperatures. Some people may need to be hospitalized for this condition. If you have a high fever, a fever that does not go away, or decreased sweating develops, call your healthcare provider right away.

QUDEXY XR can increase the level of acid in your blood (metabolic acidosis).If left untreated, metabolic acidosis can cause brittle or soft bones (osteoporosis, osteomalacia, osteopenia), kidney stones, can slow the rate of growth in children, and may possibly harm your baby if you are pregnant. Metabolic acidosis can happen with or without symptoms. Sometimes people with metabolic acidosis will:

- feel tired
- not feel hungry (loss of appetite)
- feel changes in heartbeat
- have trouble thinking clearly

Your healthcare provider should do a blood test to measure the level of acid in your blood before and during your treatment with QUDEXY XR.

If you are pregnant, you should talk to your healthcare provider about whether you have metabolic acidosis.

Like other antiepileptic drugs, QUDEXY XR may cause suicidal thoughts or actions in a very small number of people, about 1 in 500.

Call a healthcare provider right away if you have any of these symptoms, especially if they are new, worse, or worry you:

- thoughts about suicide or dying
- attempts to commit suicide
- new or worse depression
- new or worse anxiety

- feeling agitated or restless
- panic attacks
- trouble sleeping (insomnia)
- new or worse irritability

- acting aggressive, being angry, or violent
- acting on dangerous impulses
- an extreme increase in activity and talking (mania)
- other unusual changes in behavior or mood

Do not stop QUDEXY XR without first talking to a healthcare provider.

- Stopping QUDEXY XR suddenly can cause serious problems.
- Suicidal thoughts or actions can be caused by things other than medicines. If you have suicidal thoughts or actions, your healthcare provider may check for other causes.

How can I watch for early symptoms of suicidal thoughts and actions?

- Pay attention to any changes, especially sudden changes, in mood, behaviors, thoughts, or feelings.
- Keep all follow-up visits with your healthcare provider as scheduled.
- Call your healthcare provider between visits as needed, especially if you are worried about symptoms.

QUDEXY XR can harm your unborn baby.

- If you take QUDEXY XR during pregnancy, your baby has a higher risk for birth including cleft lip and cleft palate. These defects can begin early in pregnancy, even before you know you are pregnant.
- Birth defects may happen even in children born to women who are not taking any medicines and do not have other risk factors.
- There may be other medicines to treat your condition that have a lower chance of birth defects.
- All women of childbearing age should talk to their healthcare providers about using other possible treatments instead of QUDEXY XR. If the decision is made to use QUDEXY XR, you should use effective birth control (contraception) unless you are planning to become pregnant. You should talk to your healthcare provider about the best kind of birth control to use while you are taking QUDEXY XR.
- Tell your healthcare provider right away if you become pregnant while taking QUDEXY XR. You and your healthcare provider should decide if you will continue to take QUDEXY XR while you are pregnant.
- If you take QUDEXY XR during pregnancy, your baby may be smaller than expected at birth. The long-term effects of this are not known. Talk to your healthcare provider if you have any questions about this risk during pregnancy.
- Metabolic acidosis may have harmful effects on your baby. Talk to your healthcare provider if QUDEXY XR has caused metabolic acidosis during your pregnancy.
- Pregnancy Registry: If you become pregnant while taking QUDEXY XR, talk to your healthcare provider about registering with the North American Antiepileptic Drug Pregnancy Registry. You can enroll in this registry by calling 1-888-233-2334. The purpose of this registry is to collect information about the safety of QUDEXY XR and other antiepileptic drugs during pregnancy.

QUDEXY XR may decrease the density of bones when used over a long period.
QUDEXY XR may slow height increase and weight gain in children and adolescents when used over a long period.

What is QUDEXY XR?

QUDEXY XR is a prescription medicine used:

- to treat certain types of seizures (partial-onset seizures and primary generalized tonic-clonic seizures) in adults and children 2 years of age and older,
- with other medicines to treat certain types of seizures (partial-onset seizures, primary generalized tonic-clonic seizures, and seizures associated with Lennox-Gastaut syndrome) in adults and children 2 years of age and older,
- to prevent migraine headaches in adults and adolescents 12 years of age and older.

What should I tell my healthcare provider before taking QUDEXY XR?

Before taking QUDEXY XR, tell your healthcare provider about all of your medical conditions, including if you:

- have or have had depression, mood problems or suicidal thoughts or behavior
- have kidney problems, kidney stones or are getting kidney dialysis
- have a history of metabolic acidosis (too much acid in the blood)
- have liver problems
- have weak, brittle or soft bones (osteomalacia, osteoporosis, osteopenia, or decreased bone density)
- have lung or breathing problems
- have eye problems, especially glaucoma
- have diarrhea
- have a growth problem
- are on a diet high in fat and low in carbohydrates, which is called a ketogenic diet
- are having surgery
- are pregnant or plan to become pregnant
- are breastfeeding or plan to breastfeed. QUDEXY XR passes into breast milk. Breastfed babies may be sleepy or have diarrhea. It is not known if the QUDEXY XR that passes into breast milk can cause other serious harm to your baby. Talk to your healthcare provider about the best way to feed your baby if you take QUDEXY XR.

Tell your healthcare provider about all the medicines you take, including prescription and over-the-counter medicines, vitamins, and herbal supplements. QUDEXY XR and other medicines may affect each other causing side effects.

Especially tell your healthcare provider if you take:

- Valproic acid (such as DEPAKENE®or DEPAKOTE®)
- any medicines that impair or decrease your thinking, concentration, or muscle coordination
- birth control that contains hormones (such as pills, implants, patches or injections). QUDEXY XR may make your birth control less effective. Tell your healthcare provider if your menstrual bleeding changes while you are using birth control and QUDEXY XR.

Ask your healthcare provider if you are not sure if your medicine is listed above.

Know the medicines you take. Keep a list of them to show your healthcare provider and pharmacist each time you get a new medicine. Do not start a new medicine without talking with your healthcare provider.

How should I take QUDEXY XR?

- Take QUDEXY XR exactly as your healthcare provider tells you to.
- Your healthcare provider may change your dose. Do notchange your dose without talking to your healthcare provider.
- QUDEXY XR capsules may be swallowed whole or, if you cannot swallow the capsule whole, you may carefully open the QUDEXY XR capsule and sprinkle the medicine on a spoonful of soft food like applesauce.
  - Swallow the food and medicine mixture right away. Do notstore the food and medicine mixture to use later.
  - Do not crush or chew QUDEXY XR before swallowing.
- Drink plenty fluids during the day. This may help prevent kidney stones while taking QUDEXY XR.
- If you take too much QUDEXY XR, call your healthcare provider right away or go to the nearest emergency room.
- QUDEXY XR can be taken before, during, or after a meal.
- If you miss a single dose of QUDEXY XR, take it as soon as you can. If you have missed more than one dose, you should call your healthcare provider for advice.
- Do not stop taking QUDEXY XR without talking to your healthcare provider. Stopping QUDEXY XR suddenly may cause serious problems. If you have epilepsy and you stop taking QUDEXY XR suddenly, you may have seizures that do not stop. Your healthcare provider will tell you how to stop taking QUDEXY XR slowly.
- Your healthcare provider may do blood tests while you take QUDEXY XR.

What should I avoid while taking QUDEXY XR?

- You should not drink alcohol while taking QUDEXY XR. QUDEXY XR and alcohol can affect each other causing side effects such as sleepiness and dizziness.
- Do not drive a car or operate machinery until you know how QUDEXY XR affects you. QUDEXY XR can slow your thinking and motor skills and may affect vision.

What are the possible side effects of QUDEXY XR?

QUDEXY XR may cause serious side effects, including:

See " What is the most important information I should know about QUDEXY XR?"

- High blood ammonia levels.High ammonia in the blood can affect your mental activities, slow your alertness, make you feel tired, or cause vomiting. This has happened when QUDEXY XR is taken with a medicine called valproic acid (DEPAKENE®and DEPAKOTE®).
- Kidney stones.Drink plenty of fluids when taking QUDEXY XR to decrease your chances of getting kidney stones.
- Low body temperature.Taking QUDEXY XR when you are also taking valproic acid can cause a drop-in body temperature to less than 95°F, or can cause tiredness, confusion, or coma.
- Effects on thinking and alertness.QUDEXY XR may affect how you think, and cause confusion, problems with concentration, attention, memory, or speech. QUDEXY XR may cause depression or mood problems, tiredness, and sleepiness.
- Dizziness or loss of muscle coordination.
- Serious skin reactions. QUDEXY XR may cause a severe rash with blisters and peeling skin, especially around the mouth, nose, eyes, and genitals (Stevens-Johnson syndrome). QUDEXY XR may also cause a rash with blisters and peeling skin over much of the body that may cause death (toxic epidermal necrolysis). Call your healthcare provider right away if you develop a skin rash or blisters.

Call your healthcare provider right away if you have any of the symptoms above.

The most common side effects of QUDEXY XR include:

- tingling of the arms and legs (paresthesia)
- not feeling hungry
- weight loss
- nervousness
- nausea

- speech problems
- tiredness
- dizziness
- sleepiness/drowsiness
- a change in the way foods taste
- upper respiratory tract infection
- decreased feeling or sensitivity, especially in the skin

- slow reactions
- difficulty with memory
- fever
- abnormal vision
- diarrhea
- pain in the abdomen

Tell your healthcare provider about any side effect that bothers you or that does not go away.

These are not all the possible side effects of QUDEXY XR. For more information, ask your healthcare provider or pharmacist.

Call your doctor for medical advice about side effects. You may report side effects to FDA at 1-800-FDA-1088.

You may also report side effects to Upsher-Smith Laboratories, LLC at 1-855-899-9180.

How should I store QUDEXY XR?

- Store QUDEXY XR capsules at room temperature between 68°F to 77°F (20°C to 25°C).
- Keep QUDEXY XR in a tightly closed container.
- Keep QUDEXY XR dry and away from moisture.
- Keep QUDEXY XR and all medicines out of the reach of children.

General information about the safe and effective use of QUDEXY XR.

Medicines are sometimes prescribed for purposes other than those listed in a Medication Guide. Do not use QUDEXY XR for a condition for which it was not prescribed. Do not give QUDEXY XR to other people, even if they have the same symptoms that you have. It may harm them. You can ask your pharmacist or healthcare provider for information about QUDEXY XR that is written for health professionals.

What are the ingredients in QUDEXY XR?

Active ingredient:topiramate

Inactive ingredients:microcrystalline cellulose, hypromellose 2910, ethylcellulose, diethyl phthalate, titanium dioxide, black iron oxide, red iron oxide and/or yellow iron oxide, black pharmaceutical ink, and white pharmaceutical ink (200 mg only).

Distributed by: UPSHER-SMITH LABORATORIES, LLC, Maple Grove, MN 55369
Qudexy is a registered trademark of Upsher-Smith Laboratories, LLC. All other marks are property of their respective owners.
This product may be covered by one or more U.S. patent(s). See www.uslpatents.com.
For more information, go to www.upsher-smith.com or call UPSHER-SMITH LABORATORIES, LLC at 1-888-650-3789.

This Medication Guide has been approved by the U.S. Food and Drug Administration.

Revised: 3/2025

PRINCIPAL DISPLAY PANEL - 25 mg Capsule Bottle Label

NDC 0245-1071-30
Once-Daily Dosing

Qudexy®XR
(topiramate) extended-release capsules

PHARMACIST: Dispense the
Medication Guide provided
separately to each patient.

25 mg

30 Capsules
Rx only

PRINCIPAL DISPLAY PANEL - 50 mg Capsule Bottle Label

NDC 0245-1072-30

Once-Daily Dosing

Qudexy®XR
(topiramate) extended-release capsules

50 mg

PHARMACIST: Dispense the Medication Guide
provided separately to each patient.

30 Capsules
Rx only

PRINCIPAL DISPLAY PANEL - 100 mg Capsule Bottle Label

NDC 0245-1074-30

Once-Daily Dosing

Qudexy®XR
(topiramate) extended-release capsules

100 mg

PHARMACIST: Dispense the Medication
Guide provided separately to each patient.

30 Capsules
Rx only

PRINCIPAL DISPLAY PANEL - 150 mg Capsule Bottle Label

NDC 0245-1075-30

Once-Daily Dosing

Qudexy®XR
(topiramate) extended-release capsules

150 mg

PHARMACIST: Dispense the Medication
Guide provided separately to each patient.

30 Capsules
Rx only

PRINCIPAL DISPLAY PANEL - 200 mg Capsule Bottle Label

NDC 0245-1073-30

Once-Daily Dosing

Qudexy®XR
(topiramate) extended-release capsules

200 mg

PHARMACIST: Dispense the Medication
Guide provided separately to each patient.

30 Capsules
Rx only